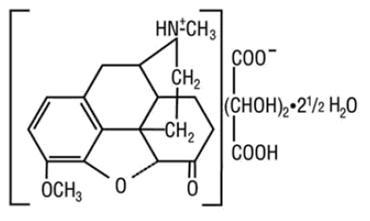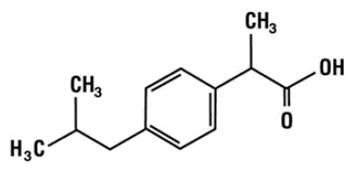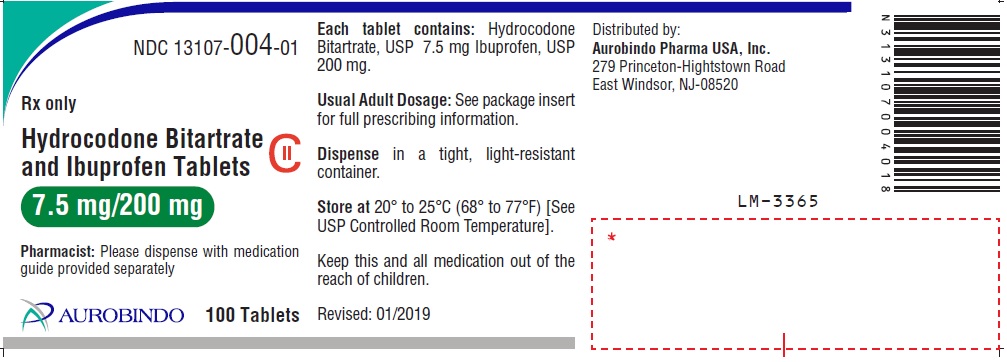 DRUG LABEL: Hydrocodone Bitartrate and Ibuprofen
NDC: 13107-004 | Form: TABLET, FILM COATED
Manufacturer: Aurolife Pharma, LLC
Category: prescription | Type: Human Prescription Drug Label
Date: 20251223
DEA Schedule: CII

ACTIVE INGREDIENTS: HYDROCODONE BITARTRATE 7.5 mg/1 1; IBUPROFEN 200 mg/1 1
INACTIVE INGREDIENTS: LACTOSE MONOHYDRATE; ANHYDROUS LACTOSE; SODIUM STARCH GLYCOLATE TYPE A POTATO; SODIUM LAURYL SULFATE; CROSCARMELLOSE SODIUM; SILICON DIOXIDE; MAGNESIUM STEARATE

HYDROCODONE BITARTRATE AND IBUPROFEN TABLETS C-II
7.5 mg/200 mg

WARNING: ADDICTION, ABUSE, AND MISUSE:RISK EVALUATION AND MITIGATION STRATEGY (REMS); LIFE-THREATENING RESPIRATORY DEPRESSION; ACCIDENTAL INGESTION; NEONATAL OPIOID WITHDRAWAL SYNDROME; CYTOCHROME P4503A4 INTERACTION; RISKS FROM CONCOMITANT USE WITH BENZODIAZEPINES OR OTHER CNS DEPRESSANTS; and SERIOUS CARDIOVASCULAR AND GASTROINTESTINAL EVENTS

WARNING: SERIOUS AND LIFE-THREATENING RISKS FROM USE OF HYDROCODONE BITARTRATE AND IBUPROFEN TABLETS

Addiction, Abuse, and Misuse

Because the use of Hydrocodone Bitartrate and Ibuprofen Tablets exposes patients and other users to the risks of opioid addiction, abuse, and misuse, which can lead to overdose and death, assess each patient’s risk prior to prescribing and reassess all patients regularly for the development of these behaviors and conditions [see Warnings].

Life-Threatening Respiratory Depression

Serious, life-threatening, or fatal respiratory depression may occur with use of Hydrocodone Bitartrate and Ibuprofen Tablets, especially during initiation or following a dose increase. To reduce the risk of respiratory depression, proper dosing and titration of Hydrocodone Bitartrate and Ibuprofen Tablets are essential [see Warnings].

Accidental Ingestion

Accidental ingestion of even one dose of Hydrocodone Bitartrate and Ibuprofen Tablets, especially by children, can result in a fatal overdose of hydrocodone (see WARNINGS).

Risks from Concomitant Use with Benzodiazepines or Other CNS Depressants

Concomitant use of opioids with benzodiazepines or other central nervous system (CNS) depressants, including alcohol, may result in profound sedation, respiratory depression, coma, and death. Reserve concomitant prescribing of Hydrocodone Bitartrate and Ibuprofen Tablets and benzodiazepines or other CNS depressants for use in patients for whom alternative treatment options are inadequate [see Warnings].

Neonatal Opioid Withdrawal Syndrome (NOWS)

Advise pregnant women using opioids for an extended period of time of the risk of Neonatal Opioid Withdrawal Syndrome, which may be life-threatening if not recognized and treated. Ensure that management by neonatology experts will be available at delivery [see Warnings].

Opioid Analgesic Risk Evaluation and Mitigation Strategy (REMS):

Healthcare providers are strongly encouraged to complete a REMS compliant education program and to counsel patients and caregivers on serious risks, safe use, and the importance of reading the Medication Guide with each prescription [see Warnings].

Cytochrome P450 3A4 Interaction

The concomitant use of Hydrocodone Bitartrate and Ibuprofen Tablets with all cytochrome P450 3A4 inhibitors may result in an increase in hydrocodone plasma concentrations, which may cause potentially fatal respiratory depression. In addition, discontinuation of a concomitantly used cytochrome P450 3A4 inducer may result in an increase in hydrocodone plasma concentration. Monitor patients taking Hydrocodone Bitartrate and Ibuprofen Tablets and any CYP3A4 inhibitor or upon discontinuation of a CYP3A4 inducer for signs and symptoms of respiratory depression and sedation (see WARNINGS: Risks of Concomitant Use or Discontinuation of Cytochrome P450 3A4 Inhibitors and Inducers, PRECAUTIONS: Drug Interactions).

Cardiovascular Thrombotic Events

Nonsteroidal anti-inflammatory drugs (NSAIDs) cause an increased risk of serious cardiovascular thrombotic events, including myocardial infarction and stroke, which can be fatal. This risk may occur early in treatment and may increase with duration of use (see WARNINGS: Cardiovascular Thrombotic Events).

Hydrocodone Bitartrate and Ibuprofen Tablets are contraindicated in the setting of coronary artery bypass graft (CABG) surgery (see CONTRAINDICATIONS, WARNINGS: Cardiovascular Thrombotic Events).

Gastrointestinal Bleeding, Ulceration, and Perforation

NSAIDs cause an increased risk of serious gastrointestinal (GI) adverse events including bleeding, ulceration, and perforation of the stomach or intestines, which can be fatal. These events can occur at any time during use and without warning symptoms. Elderly patients and patients with a prior history of peptic ulcer disease and/or GI bleeding are at greater risk for serious GI events (see WARNINGS: Gastrointestinal Bleeding, Ulceration, and Perforation).

DESCRIPTION

Each hydrocodone bitartrate and ibuprofen tablet contains:
Hydrocodone Bitartrate, USP 7.5 mg
Ibuprofen, USP 200 mg
Hydrocodone Bitartrate and Ibuprofen Tablets are supplied in a fixed combination tablet form for oral administration. Hydrocodone Bitartrate and Ibuprofen Tablets combines the opioid agonist agent, hydrocodone bitartrate, with the nonsteroidal anti-inflammatory (NSAID) agent, ibuprofen.
Hydrocodone bitartrate is a semisynthetic opioid agonist. Its chemical name is: 4,5 α-epoxy-3-methoxy-17-methylmorphinan-6-one tartrate (1:1) hydrate (2:5). Its chemical formula is: C18H21NO3•C4H6O6•2½H2O, and the molecular weight is 494.50. Its structural formula is:

Ibuprofen is a non-steroidal anti-inflammatory agent [non-selective COX inhibitor] with analgesic and antipyretic properties. Its chemical name is: (±)-2-(p-isobutylphenyl) propionic acid. Its chemical formula is: C13H18O2, and the molecular weight is: 206.29. Its structural formula is:

Inactive ingredients in Hydrocodone Bitartrate and Ibuprofen tablets include: anhydrous lactose, colloidal silicon dioxide, croscarmellose sodium, lactose monohydrate, magnesium stearate, sodium starch glycolate, sodium lauryl sulfate, polysorbate 80, hypromellose, titanium dioxide and polyethylene glycol.

CLINICAL PHARMACOLOGY

Mechanism of Action
Hydrocodone Component
Hydrocodone is a full opioid agonist with relative selectivity for the mu-opioid receptor, although it can interact with other opioid receptors at higher doses. The principal therapeutic action of hydrocodone is analgesia. Like all full opioid agonists, there is no ceiling effect for analgesia with hydrocodone. Clinically, dosage is titrated to provide adequate analgesia and may be limited by adverse reactions, including respiratory and CNS depression.
The precise mechanism of the analgesic action is unknown. However, specific CNS opioid receptors for endogenous compounds with opioid-like activity have been identified throughout the brain and spinal cord and are thought to play a role in the analgesic effects of this drug.
Ibuprofen Component
Ibuprofen has analgesic, anti-inflammatory, and antipyretic properties.
The mechanism of action, like that of other NSAIDs, is not completely understood, but involves inhibition of cyclooxygenase (COX-1 and COX-2).
Ibuprofen is a potent inhibitor of prostaglandin synthesis in vitro. Ibuprofen concentrations reached during therapy have produced in vivo effects. Prostaglandins sensitize afferent nerves and potentiate the action of bradykinin in inducing pain in animal models. Prostaglandins are mediators of inflammation. Because ibuprofen is an inhibitor of prostaglandin synthesis, its mode of action may be due to a decrease of prostaglandins in peripheral tissues.
Pharmacodynamics
Effects on the Central Nervous System
Hydrocodone produces respiratory depression by direct action on brain stem respiratory centers. The respiratory depression involves a reduction in the responsiveness of the brain stem respiratory centers to both increases in carbon dioxide tension and electrical stimulation.
Hydrocodone causes miosis, even in total darkness. Pinpoint pupils are a sign of opioid overdose but are not pathognomonic (e.g., pontine lesions of hemorrhagic or ischemic origins may produce similar findings). Marked mydriasis rather than miosis may be seen due to hypoxia in overdose situations.
Effects on the Gastrointestinal Tract and Other Smooth Muscle
Hydrocodone causes a reduction in motility associated with an increase in smooth muscle tone in the antrum of the stomach and duodenum. Digestion of food in the small intestine is delayed and propulsive contractions are decreased. Propulsive peristaltic waves in the colon are decreased, while tone may be increased to the point of spasm, resulting in constipation. Other opioid- induced effects may include a reduction in biliary and pancreatic secretions, spasm of sphincter of Oddi, and transient elevations in serum amylase, and opioid-induced esophageal dysfunction (OIED).
Effects on the Cardiovascular System
Hydrocodone produces peripheral vasodilation, which may result in orthostatic hypotension or syncope. Manifestations of histamine release and/or peripheral vasodilation may include pruritus, flushing, red eyes, sweating, and/or orthostatic hypotension.
Effects on the Endocrine System
Opioids inhibit the secretion of adrenocorticotropic hormone (ACTH), cortisol, and luteinizing hormone (LH) in humans (see ADVERSE REACTIONS: Post marketing Experience). They also stimulate prolactin, growth hormone (GH) secretion, and pancreatic secretion of insulin and glucagon.
Use of opioids for an extended period of time may influence the hypothalamic-pituitary-gonadal axis, leading to androgen deficiency that may manifest as low libido, impotence, erectile dysfunction, amenorrhea, or infertility. The causal role of opioids in the clinical syndrome of hypogonadism is unknown because the various medical, physical, lifestyle, and psychological stressors that may influence gonadal hormone levels have not been adequately controlled for in studies conducted to date (see ADVERSE REACTIONS: Post marketing Experience).
Effects on the Immune System
Opioids have been shown to have a variety of effects on components of the immune system in both in vitro and animal models. The clinical significance of these findings is unknown. Overall, the effects of opioids appear to be modestly immunosuppressive.
Concentration-Efficacy Relationships
The minimum effective analgesic concentration will vary widely among patients, especially among patients who have been previously treated with extended-release agonist opioids. The minimum effective analgesic concentration of hydrocodone for any individual patient may increase over time due to an increase in pain, the development of a new pain syndrome, and/or the development of analgesic tolerance (seeDOSAGE AND ADMINISTRATION).
Concentration-Adverse Reaction Relationships
There is a relationship between increasing hydrocodone plasma concentration and increasing frequency of dose-related opioid adverse reactions such as nausea, vomiting, CNS effects, and respiratory depression. In opioid-tolerant patients, the situation may be altered by the development of tolerance to opioid-related adverse reactions (see DOSAGE AND ADMINISTRATION).
In a healthy volunteer study, ibuprofen 400 mg given once daily, administered 2 hours prior to immediate-release aspirin (81 mg) for 6 days, showed an interaction with the antiplatelet activity of aspirin as measured by % serum thromboxane 82 (TxB2) inhibition at 24 hours following the day-6 aspirin dose [53%]. An interaction was still observed, but minimized, when ibuprofen 400 mg given once-daily was administered as early as 8 hours prior to the immediate-release aspirin dose [90.7%]. However, there was no interaction with the antiplatelet activity of aspirin when ibuprofen 400 mg, given once daily, was administered 2 hours after (but not concomitantly, 15 min, or 30 min after) the immediate-release aspirin dose [99.2%].

In another study, where immediate-release aspirin 81 mg was administered once daily with ibuprofen 400 mg given three times daily (1 , 7, and 13 hours post-aspirin dose) for 10 consecutive days, the mean % serum thromboxane 82 (TxB2) inhibition suggested no interaction with the antiplatelet activity of aspirin [98.3%]. However, there were individual subjects with serum TxB2 inhibition below 95%, with the lowest being 90.2%.

When a similarly designed study was conducted with enteric-coated aspirin, where healthy subjects were administered enteric-coated aspirin 81 mg once daily for 6 days and ibuprofen 400 mg three times daily (2, 7 and 12 h post-aspirin dose) for 6 days, there was an interaction with the antiplatelet activity at 24 hours following the day-6 aspirin dose [67%]. [See Precautions/Drug Interactions].
Pharmacokinetics

Absorption
After oral dosing with the Hydrocodone Bitartrate and Ibuprofen Tablets, a peak hydrocodone plasma level of 27 ng/mL is achieved at 1.7 hours, and a peak ibuprofen plasma level of 30 mcg/mL is achieved at 1.8 hours. The effect of food on the absorption of either component from the Hydrocodone Bitartrate and Ibuprofen Tablets tablet has not been established.
Distribution
Ibuprofen is highly protein-bound (99%) like most other non-steroidal anti-inflammatory agents. Although the extent of protein binding of hydrocodone in human plasma has not been definitely determined, structural similarities to related opioid analgesics suggest that hydrocodone is not extensively protein bound. As most agents in the 5-ring morphinan group of semi-synthetic opioids bind plasma protein to a similar degree (range 19% [hydromorphone] to 45% [oxycodone]), hydrocodone is expected to fall within this range.
Elimination
Metabolism
Hydrocodone exhibits a complex pattern of metabolism, including O-demethylation, N demethylation, and 6-keto reduction to the corresponding 6-α-and 6-β-hydroxy metabolites. Hydromorphone, a potent opioid, is formed from the O-demethylation of hydrocodone and contributes to the total analgesic effect of hydrocodone. The O- and N- demethylation processes are mediated by separate P-450 isoenzymes: CYP2D6 and CYP3A4, respectively.
Ibuprofen is present in this product as a racemate, and following absorption it undergoes interconversion in the plasma from the R-isomer to the S-isomer. Both the R- and S- isomers are metabolized to two primary metabolites: (+)-2-4'-(2hydroxy-2-methyl-propyl) phenyl propionic acid and (+)-2-4'-(2carboxypropyl) phenyl propionic acid, both of which circulate in the plasma at low levels relative to the parent.
Excretion
Hydrocodone and its metabolites are eliminated primarily in the kidneys, with a mean plasma half-life of 4.5 hours. Ibuprofen is excreted in the urine, 50% to 60% as metabolites and approximately 15% as unchanged drug and conjugate. The plasma half-life is 2.2 hours.
Specific Populations
No significant pharmacokinetic differences based on age or gender have been demonstrated. The pharmacokinetics of hydrocodone and ibuprofen from Hydrocodone Bitartrate and Ibuprofen Tablets have not been evaluated in children.
Renal Impairment
The effect of renal insufficiency on the pharmacokinetics of the Hydrocodone Bitartrate and Ibuprofen Tablets dosage form has not been determined.
Drug Interaction Studies
Aspirin
When NSAIDs were administered with aspirin, the protein binding of NSAIDs were reduced, although the clearance of free NSAID was not altered. The clinical significance of this interaction is not known (see PRECAUTIONS: Drug Interactions).

CLINICAL STUDIES

In single-dose studies of post-surgical pain (abdominal, gynecological, orthopedic), 940 patients were studied at doses of one or two tablets. Hydrocodone Bitartrate and Ibuprofen Tablets produced greater efficacy than placebo and each of its individual components given at the same dose. No advantage was demonstrated for the two-tablet dose.

INDICATIONS AND USAGE

Hydrocodone Bitartrate and Ibuprofen Tablets are indicated for the short-term management of acute pain severe enough to require an opioid analgesic and for which alternative treatments are inadequate.
Limitations of Use
Carefully consider the potential benefits and risks of Hydrocodone Bitartrate and Ibuprofen Tablets and other treatment options before deciding to use Hydrocodone Bitartrate and Ibuprofen Tablets Use the lowest effective dosage for the shortest duration consistent with individual patient treatment goals (see WARNINGS: Cardiovascular Thrombotic Events, Gastrointestinal Bleeding, Ulceration, and Perforation). Do not use Hydrocodone Bitartrate and Ibuprofen Tablets for the treatment of conditions such as osteoarthritis or rheumatoid arthritis.
Because of the risks of addiction, abuse, misuse, overdose and death, which can occur at any dosage or duration and persist over the course of therapy (seeWARNINGS), reserve opioid analgesics, including Hydrocodone Bitartrate and Ibuprofen Tablets for use in patients for whom alternative treatment options are ineffective, not tolerated, or would be otherwise inadequate to provide sufficient management of pain.

CONTRAINDICATIONS

Hydrocodone Bitartrate and Ibuprofen Tablets are contraindicated in patients with:

- Significant respiratory depression (see WARNINGS: Life-Threatening Respiratory Depression).
- Acute or severe bronchial asthma in an unmonitored setting or in the absence of resuscitative equipment (see WARNINGS: Life-Threatening Respiratory Depression in Patients with Chronic Pulmonary Disease or in Elderly, Cachectic, or Debilitated Patients).
- Known or suspected gastrointestinal obstruction, including paralytic ileus (see WARNINGS: Risks of Use in Patients with Gastrointestinal Conditions).
- Known hypersensitivity (e.g., anaphylactic reactions, serious skin reactions) to hydrocodone, ibuprofen, or any components of the drug product (see WARNINGS: Anaphylactic Reactions, Serious Skin Reactions). Patients known to be hypersensitive to other opioids may exhibit cross-sensitivity to hydrocodone.
- History of asthma, urticaria, or other allergic-type reactions after taking aspirin or other NSAIDs. Severe, sometimes fatal, anaphylactic reactions to NSAIDs have been reported in such patients (see WARNINGS: Anaphylactic Reactions, Exacerbation of Asthma Related to Aspirin Sensitivity).
- In the setting of coronary artery bypass graft (CABG) surgery (see WARNINGS: Cardiovascular Thrombotic Events).

WARNINGS

Hydrocodone Component

Addiction, Abuse, and Misuse
Hydrocodone Bitartrate and Ibuprofen Tablets contains hydrocodone, a Schedule II controlled substance. As an opioid- containing product, Hydrocodone Bitartrate and Ibuprofen Tablets exposes users to the risks of addiction, abuse, and misuse (see DRUG ABUSE AND DEPENDENCE).

Although the risk of addiction in any individual is unknown, it can occur in patients appropriately prescribed Hydrocodone Bitartrate and Ibuprofen Tablets. Addiction can occur at recommended dosages and if the drug is misused or abused.The risk of opioid-related overdose or overdose-related death is increased with higher opioid doses, and this risk persists over the course of therapy. In post-marketing studies, addiction, abuse, misuse, and fatal and non-fatal opioid overdose were observed in patients with long-term opioid use [ADVERSE REACTIONS].

Assess each patient’s risk for opioid addiction, abuse, or misuse prior to prescribing Hydrocodone Bitartrate and Ibuprofen Tablets, and reassess all patients receiving Hydrocodone Bitartrate and Ibuprofen Tablets for the development of these behaviors and conditions. Risks are increased in patients with a personal or family history of substance abuse (including drug or alcohol abuse or addiction) or mental illness (e.g., major depression). The potential for these risks should not, however, prevent the proper management of pain in any given patient. Patients at increased risk may be prescribed opioid such as Hydrocodone Bitartrate and Ibuprofen Tablets, but use in such patients necessitates intensive counseling about the risks and proper use of Hydrocodone Bitartrate and Ibuprofen Tablets along with frequent reevaluation for signs of addiction, abuse, and misuse.

Consider recommending or prescribing an opioid overdose reversal agent (WARNINGS, DOSAGE AND ADMINISTRATION.

Opioids are sought for nonmedical use and are subject to diversion from legitimate prescribed use. Consider these risks when prescribing or dispensing Hydrocodone Bitartrate and Ibuprofen Tablets. Strategies to reduce these risks include prescribing the drug in the smallest appropriate quantity and advising the patient careful storage of the drug during the course of treatment and proper disposal of unused drug. Contact local state professional licensing board or state-controlled substances authority for information on how to prevent and detect abuse or diversion of this product.
Life-Threatening Respiratory Depression
Serious, life-threatening, or fatal respiratory depression has been reported with the use of opioids, even when used as recommended. Respiratory depression, if not immediately recognized and treated, may lead to respiratory arrest and death. Management of respiratory depression may include close observation, supportive measures, and use of opioid overdose reversal agents, depending on the patient’s clinical status (see OVERDOSAGE). Carbon dioxide (CO2) retention from opioid-induced respiratory depression can exacerbate the sedating effects of opioids.
While serious, life-threatening, or fatal respiratory depression can occur at any time during the use of Hydrocodone Bitartrate and Ibuprofen Tablets, the risk is greatest during the initiation of therapy or following a dosage increase.
To reduce the risk of respiratory depression, proper dosing and titration of Hydrocodone Bitartrate and Ibuprofen Tablets are essential (see DOSAGE AND ADMINISTRATION). Overestimating the Hydrocodone Bitartrate and Ibuprofen Tablets dosage when converting patients from another opioid product can result in a fatal overdose with the first dose.
Accidental ingestion of even one dose of Hydrocodone Bitartrate and Ibuprofen Tablets, especially by children, can result in respiratory depression and death due to an overdose of Hydrocodone Bitartrate and Ibuprofen Tablets.

Educate patients and caregivers on how to recognize respiratory depression and emphasize the importance of calling 911 or getting emergency medical help right away in the event of a known or suspected overdose (see PRECAUTIONS, Information for Patients).

Opioids can cause sleep-related breathing disorders including central sleep apnea (CSA) and sleep-related hypoxemia. Opioid use increases the risk of CSA in a dose-dependent fashion. In patients who present with CSA, consider decreasing the opioid dosage using best practices for opioid taper (see Dosage and Administration).
Risks from Concomitant Use with Benzodiazepines or Other CNS Depressants

Profound sedation, respiratory depression, coma, and death may result from the concomitant use of Hydrocodone Bitartrate and Ibuprofen Tablets with benzodiazepines or other CNS depressants (e.g., non-benzodiazepine sedatives/hypnotics, anxiolytics, tranquilizers, muscle relaxants, general anesthetics, antipsychotics, gabapentinoids [ gabapentin or pregabalin] other opioids,). Because of these risks, reserve concomitant prescribing of these drugs for use in patients for whom alternative treatment options are inadequate.

Observational studies have demonstrated that concomitant use of opioid analgesics and benzodiazepines increases the risk of drug-related mortality compared to use of opioid analgesics alone. Because of similar pharmacological properties, it is reasonable to expect similar risk with the concomitant use of other CNS depressant drugs with opioid analgesics (see PRECAUTIONS: Drug Interactions).

If the decision is made to prescribe a benzodiazepine or other CNS depressant concomitantly with an opioid analgesic, prescribe the lowest effective dosages and minimum durations of concomitant use. In patients already receiving an opioid analgesic, prescribe a lower initial dose of the benzodiazepine or other CNS depressant than indicated in the absence of an opioid, and titrate based on clinical response. If an opioid analgesic is initiated in a patient already taking a benzodiazepine or other CNS depressant, prescribe a lower initial dose of the opioid analgesic, and titrate based on clinical response. Inform patients and caregivers of this potential interaction, educate them on the signs and symptoms of respiratory depression (including sedation).
If concomitant use is warranted, consider recommending or prescribing an opioid overdose reversal agent (see WARNINGS, DOSAGE AND ADMINISTRATION, and OVERDOSAGE)

Advise both patients and caregivers about the risks of respiratory depression and sedation when Hydrocodone Bitartrate and Ibuprofen Tablets are used with benzodiazepines or other CNS depressants (including alcohol and illicit drugs). Advise patients not to drive or operate heavy machinery until the effects of concomitant use of the benzodiazepine or other CNS depressant have been determined. Screen patients for risk of substance use disorders, including opioid abuse and misuse, and warn them of the risk for overdose and death associated with the use of additional CNS depressants including alcohol and illicit drugs (see PRECAUTIONS: Drug Interactions, Information for Patients).

Neonatal Opioid Withdrawal Syndrome

Use of Hydrocodone Bitartrate and Ibuprofen Tablets for an extended period of time during pregnancy can result in withdrawal in the neonate. Neonatal opioid withdrawal syndrome, unlike opioid withdrawal syndrome in adults, may be life-threatening if not recognized and treated, and requires management according to protocols developed by neonatology experts. Observe newborns for signs of neonatal opioid withdrawal syndrome and manage accordingly. Advise pregnant women using opioids for an extended period of time of the risk of neonatal opioid withdrawal syndrome and ensure that appropriate treatment will be available (see PRECAUTIONS: Pregnancy, Information for Patients).

Opioid Analgesic Risk Evaluation and Mitigation Strategy (REMS):
To ensure that the benefits of opioid analgesics outweigh the risks of addiction, abuse, and misuse, the Food and Drug Administration (FDA) has required a Risk Evaluation and Mitigation Strategy (REMS) for these products. Under the requirements of the REMS, drug companies with approved opioid analgesic products must make REMS-compliant education programs available to healthcare providers.
Healthcare providers are strongly encouraged to do all of the following:

• Complete a REMS-compliant education program offered by an accredited provider of continuing education (CE) or another education program that includes all the elements of the FDA Education Blueprint for Health Care Providers Involved in the Management or Support of Patients with Pain.
• Discuss the safe use, serious risks, and proper storage and disposal of opioid analgesics with patients and/or their caregivers every time these medicines are prescribed. The Patient Counseling Guide (PCG) can be obtained at this link: www.fda.gov/OpioidAnalgesicREMSPCG.
• Emphasize to patients and their caregivers the importance of reading the Medication Guide that they will receive from their pharmacist every time an opioid analgesic is dispensed to them.
• Consider using other tools to improve patient, household, and community safety, such as patient- prescriber agreements that reinforce patient- prescriber responsibilities.
To obtain further information on the opioid analgesic REMS and for a list of accredited REMS

CME/CE, call 800-503-0784, or log on to www.opioidanalgesicrems.com. The FDA Blueprint can be found at www.fda.gov/OpioidAnalgesicREMSBlueprint.

Risks of Concomitant Use or Discontinuation of Cytochrome P450 3A4 Inhibitors and Inducers

Concomitant use of Hydrocodone Bitartrate and Ibuprofen Tablets with a CYP3A4 inhibitor, such as macrolide antibiotics (e.g., erythromycin), azole-antifungal agents (e.g., ketoconazole), and protease inhibitors (e.g., ritonavir), may increase plasma concentrations of hydrocodone and prolong opioid adverse reactions, which may cause potentially fatal respiratory depression (see WARNINGS: Life- Threatening Respiratory Depression), particularly when an inhibitor is added after a stable dose of Hydrocodone Bitartrate and Ibuprofen Tablets are achieved. Similarly, discontinuation of a CYP3A4 inducer, such as rifampin, carbamazepine, and phenytoin, in Hydrocodone Bitartrate and Ibuprofen Tablets -treated patients may increase hydrocodone plasma concentrations and prolong opioid adverse reactions. When using Hydrocodone Bitartrate and Ibuprofen Tablets with CYP3A4 inhibitors or discontinuing CYP3A4 inducers in Hydrocodone Bitartrate and Ibuprofen Tablets treated patients, evaluate patients at frequent intervals and consider dosage reduction of Hydrocodone Bitartrate and Ibuprofen Tablets until stable drug effects are achieved (see DOSAGE AND ADMINISTRATION, PRECAUTIONS: Drug Interactions).

Concomitant use of Hydrocodone Bitartrate and Ibuprofen Tablets with CYP3A4 inducers or discontinuation of a CYP3A4 inhibitor could decrease hydrocodone plasma concentrations, decrease opioid efficacy or, possibly, lead to a withdrawal syndrome in a patient who had developed physical dependence to hydrocodone. When using Hydrocodone Bitartrate and Ibuprofen Tablets with CYP3A4 inducers or discontinuing CYP3A4 inhibitors, monitor patients closely at frequent intervals and consider increasing the opioid dosage if needed to maintain adequate analgesia or if symptoms of opioid withdrawal occur (see DOSAGE AND ADMINISTRATION, PRECAUTIONS: Drug Interactions).

Opioid Induced Hyperalgesia and Allodynia
Opioid-Induced Hyperalgesia (OIH) occurs when an opioid analgesic paradoxically causes an increase in pain, or an increase in sensitivity to pain. This condition differs from tolerance, which is the need for increasing doses of opioids to maintain a defined effect [see Dependence]. Symptoms of OIH include (but may not be limited to) increased levels of pain upon opioid dosage increase, decreased levels of pain upon opioid dosage decrease, or pain from ordinarily non-painful stimuli (allodynia). These symptoms may suggest OIH only if there is no evidence of underlying disease progression, opioid tolerance, opioid withdrawal, or addictive behavior.
Cases of OIH have been reported, both with short-term and longer-term use of opioid analgesics. Though the mechanism of OIH is not fully understood, multiple biochemical pathways have been implicated. Medical literature suggests a strong biologic plausibility between opioid analgesics and OIH and allodynia. If a patient is suspected to be experiencing OIH, carefully consider appropriately decreasing the dose of the current opioid analgesic, or opioid rotation (safely switching the patient to a different opioid moiety) [see Dosage and Administration, Warnings].
Patient Access to an Opioid Overdose Reversal Agent for the Emergency Treatment of Opioid Overdose

Inform patients and caregivers about opioid overdose reversal agents (e.g., naloxone, nalmefene). Discuss the importance of having access to an opioid overdose reversal agent, especially if the patient has risk factors for overdose (e.g., concomitant use of CNS depressants, a history of opioid use disorder, or prior opioid overdose) or if there are household members (including children) or other close contacts at risk for accidental ingestion or opioid overdose. The presence of risk factors for overdose should not prevent the management of pain in any patient [see WARNINGS].
Discuss the options for obtaining an opioid overdose reversal agent (e.g., prescription, over-the-counter, or as part of a community-based program).
There are important differences among the opioid overdose reversal agents, such as route of administration, product strength, approved patient age range, and pharmacokinetics. Be familiar with these differences, as outlined in the approved labeling for those products, prior to recommending or prescribing such an agent.
Educate patients and caregivers on how to recognize respiratory depression, and how to use an opioid overdose reversal agent for the emergency treatment of opioid overdose. Emphasize the importance of calling 911 or getting emergency medical help, even if an opioid overdose reversal agent is administered [see WARNINGS, OVERDOSAGE].

Life-Threatening Respiratory Depression in Patients with Chronic Pulmonary Disease or in Elderly, Cachectic, or Debilitated Patients

The use of Hydrocodone Bitartrate and Ibuprofen Tablets in patients with acute or severe bronchial asthma in an unmonitored setting or in the absence of resuscitative equipment is contraindicated.

Patients with Chronic Pulmonary Disease: Hydrocodone Bitartrate and Ibuprofen Tablets -treated patients with significant chronic obstructive pulmonary disease or cor pulmonale, and those with a substantially decreased respiratory reserve, hypoxia, hypercapnia, or pre-existing respiratory depression are at increased risk of decreased respiratory drive including apnea, even at recommended dosages of Hydrocodone Bitartrate and Ibuprofen Tablets (see WARNINGS: Life-Threatening Respiratory Depression).

Elderly, Cachectic, or Debilitated Patients: Life-threatening respiratory depression is more likely to occur in elderly, cachectic, or debilitated patients because they may have altered pharmacokinetics or altered clearance compared to younger, healthier patients (see WARNINGS: Life-Threatening Respiratory Depression).

Regularly evaluate patients, particularly when initiating and titrating Hydrocodone Bitartrate and Ibuprofen Tablets and when Hydrocodone Bitartrate and Ibuprofen Tablets are given concomitantly with other drugs that depress respiration (see WARNINGS: Life-Threatening Respiratory Depression). Alternatively, consider the use of non- opioid analgesics in these patients.

Adrenal Insufficiency
Cases of adrenal insufficiency have been reported with opioid use, more often following greater than one month of use. Presentation of adrenal insufficiency may include non-specific symptoms and signs including nausea, vomiting, anorexia, fatigue, weakness, dizziness, and low blood pressure. If adrenal insufficiency is suspected, confirm the diagnosis with diagnostic testing as soon as possible. If adrenal insufficiency is diagnosed, treat with physiologic replacement doses of corticosteroids. Wean the patient off of the opioid to allow adrenal function to recover and continue corticosteroid treatment until adrenal function recovers. Other opioids may be tried as some cases reported use of a different opioid without recurrence of adrenal insufficiency. The information available does not identify any particular opioids as being more likely to be associated with adrenal insufficiency.

Severe Hypotension
Hydrocodone Bitartrate and Ibuprofen Tablets may cause severe hypotension including orthostatic hypotension and syncope in ambulatory patients. There is increased risk in patients whose ability to maintain blood pressure has already been compromised by a reduced blood volume or concurrent administration of certain CNS depressant drugs (e.g., phenothiazines or general anesthetics) (see PRECAUTIONS: Drug Interactions). Regularly evaluate these patients for signs of hypotension after initiating or titrating the dosage of Hydrocodone Bitartrate and Ibuprofen Tablets. In patients with circulatory shock, Hydrocodone Bitartrate and Ibuprofen Tablets may cause vasodilation that can further reduce cardiac output and blood pressure. Avoid the use of Hydrocodone Bitartrate and Ibuprofen Tablets in patients with circulatory shock.

Risks of Use in Patients with Increased Intracranial Pressure, Brain Tumors, Head Injury, or Impaired Consciousness
In patients who may be susceptible to the intracranial effects of CO2 retention (e.g., those with evidence of increased intracranial pressure or brain tumors), Hydrocodone Bitartrate and Ibuprofen Tablets may reduce respiratory drive, and the resultant CO2 retention can further increase intracranial pressure. Monitor such patients for signs of sedation and respiratory depression, particularly when initiating therapy with Hydrocodone Bitartrate and Ibuprofen Tablets.
Opioids may also obscure the clinical course in a patient with a head injury. Avoid the use of Hydrocodone Bitartrate and Ibuprofen Tablets in patients with impaired consciousness or coma.
Risks of Gastrointestinal Conditions
Hydrocodone Bitartrate and Ibuprofen Tablets are contraindicated in patients with known or suspected gastrointestinal obstruction, including paralytic ileus.
The hydrocodone in Hydrocodone Bitartrate and Ibuprofen Tablets may cause spasm of the sphincter of Oddi. Opioids may cause increases in serum amylase. Regularly evaluate patients with biliary tract disease, including acute pancreatitis, for worsening symptoms.
Cases of opioid-induced esophageal dysfunction (OIED) have been reported in patients taking opioids. The risk of OIED may increase as the dose and/or duration of opioids increases. Regularly evaluate patients for
signs and symptoms of OIED (e.g., dysphagia, regurgitation, non-cardiac chest pain), and if necessary, adjust opioid therapy as clinically appropriate [see CLINICAL PHARMACOLOGY].

Increased Risk of Seizures in Patients with Seizure Disorders

The hydrocodone in Hydrocodone Bitartrate and Ibuprofen Tablets may increase the frequency of seizures in patients with seizure disorders, and may increase the risk of seizures occurring in other clinical settings associated with seizures. Regularly evaluate patients with a history of seizure disorders for worsened seizure control during Hydrocodone Bitartrate and Ibuprofen Tablets therapy.

Withdrawal
Do not abruptly discontinue Hydrocodone Bitartrate and Ibuprofen Tablets in a patient physically dependent on opioids. When discontinuing Hydrocodone Bitartrate and Ibuprofen Tablets in a physically dependent patient, gradually taper the dosage. Rapid tapering of Hydrocodone Bitartrate and Ibuprofen Tablets in a patient physically dependent on opioids may lead to a withdrawal syndrome and return of pain [see Dosage and Administration, Drug Abuse and Dependence].
Additionally, avoid the use of mixed agonist/antagonist (e.g., pentazocine, nalbuphine, and butorphanol) or partial agonist (e.g., buprenorphine) analgesics in patients who are receiving a full opioid agonist analgesic, including Hydrocodone Bitartrate and Ibuprofen Tablets. In these patients, mixed agonist/antagonist and partial agonist analgesics may reduce the analgesic effect and/or precipitate withdrawal symptoms (see PRECAUTIONS/Drug Interactions).

Risks of Driving and Operating Machinery
Hydrocodone Bitartrate and Ibuprofen Tablets may impair the mental or physical abilities needed to perform potentially hazardous activities such as driving a car or operating machinery. Warn patients not to drive or operate dangerous machinery unless they are tolerant to the effects of Hydrocodone Bitartrate and Ibuprofen Tablets and know how they will react to the medication (see PRECAUTIONS: Information for Patients).

Ibuprofen Component

Cardiovascular Thrombotic Events

Clinical trials of several COX-2 selective and nonselective NSAIDs of up to three years duration have shown an increased risk of serious cardiovascular (CV) thrombotic events, including myocardial infarction (MI), and stroke, which can be fatal. Based on available data, it is unclear that the risk for CV thrombotic events is similar for all NSAIDs. The relative increase in serious CV thrombotic events over baseline conferred by NSAID use appears to be similar in those with and without known CV disease or risk factors for CV disease. However, patients with known CV disease or risk factors had a higher absolute incidence of excess serious CV thrombotic events, due to their increased baseline rate. Some observational studies found that this increased risk of serious CV thrombotic events began as early as the first weeks of treatment. The increase in CV thrombotic risk has been observed most consistently at higher doses.

To minimize the potential risk for an adverse CV event in NSAID-treated patients, use the lowest effective dose for the shortest duration possible. Physicians and patients should remain alert for the development of such events, throughout the entire treatment course, even in the absence of previous CV symptoms. Patients should be informed about the symptoms of serious CV events and the steps to take if they occur.

There is no consistent evidence that concurrent use of aspirin mitigates the increased risk of serious CV thrombotic events associated with NSAID use. The concurrent use of aspirin and an NSAID, such as ibuprofen, increases the risk of serious gastrointestinal (GI) events (see WARNINGS: Gastrointestinal Bleeding, Ulceration, and Perforation).

Status Post Coronary Artery Bypass Graft (CABG) Surgery

Two large controlled clinical trials of a COX-2 selective NSAID for the treatment of pain in the first 10-14 days following CABG surgery found an increased incidence of myocardial infarction and stroke. NSAIDs are contraindicated in the setting of CABG (see CONTRAINDICATIONS).

Post-MI Patients
Observational studies conducted in the Danish National Registry have demonstrated that patients treated with NSAIDs in the post-MI period were at increased risk of reinfarction, CV-related death, and all-cause mortality beginning in the first week of treatment. In this same cohort, the incidence of death in the first year post-MI was 20 per 100 person years in NSAID-treated patients compared to 12 per 100 person years in non-NSAID exposed patients.

Although the absolute rate of death declined somewhat after the first year post-MI, the increased relative risk of death in NSAID users persisted over at least the next four years of follow-up.

Avoid the use of hydrocodone bitartrate and ibuprofen tablets in patients with a recent MI unless the benefits are expected to outweigh the risk of recurrent CV thrombotic events. If hydrocodone bitartrate and ibuprofen tablets are used in patients with a recent MI, monitor patients for signs of cardiac ischemia.

Gastrointestinal Bleeding, Ulceration, and Perforation
NSAIDs, including ibuprofen, cause serious gastrointestinal (GI) adverse events including inflammation, bleeding, ulceration, and perforation of the esophagus, stomach, small intestine, or large intestine, which can be fatal. These serious adverse events can occur at any time, with or without warning symptoms, in patients treated with Hydrocodone Bitartrate and Ibuprofen Tablets. Only one in five patients who develop a serious upper GI adverse event on NSAID therapy is symptomatic. Upper GI ulcers, gross bleeding, or perforation caused by NSAIDs occurred in approximately 1% of patients treated for 3-6 months, and in about 2%-4% of patients treated for one year. However, even short-term NSAID therapy is not without risk.

Risk Factors for GI Bleeding, Ulceration, and Perforation
Patients with a prior history of peptic ulcer disease and/or gastrointestinal bleeding who used NSAIDs had a greater than 10-fold increased risk for developing a GI bleed compared to patients without these risk factors. Other factors that increase the risk for GI bleeding in patients treated with NSAIDs include longer duration of NSAID therapy; concomitant use of oral corticosteroids, aspirin, anticoagulants, or selective serotonin reuptake inhibitors (SSRIs); smoking; use of alcohol; older age; and poor general health status. Most post marketing reports of fatal GI events occurred in elderly or debilitated patients. Additionally, patients with advanced liver disease and/or coagulopathy are at increased risk for GI bleeding.

Strategies to Minimize the GI Risks in NSAID-treated patients:
• Use the lowest effective dosage for the shortest possible duration.
• Avoid administration of more than one NSAID at a time.
• Avoid use in patients at higher risk unless benefits are expected to outweigh the increased risk of bleeding. For high risk patients, as well as those with active GI bleeding, consider alternate therapies other than NSAIDs.
• Remain alert for signs and symptoms of GI ulceration and bleeding during NSAID therapy.
• If a serious GI adverse event is suspected, promptly initiate evaluation and treatment, and discontinue hydrocodone bitartrate and ibuprofen tablets until a serious GI adverse event is ruled out.

• In the setting of concomitant use of low-dose aspirin for cardiac prophylaxis, monitor patients more closely for evidence of GI bleeding (see PRECAUTIONS: Drug Interactions).

Hepatotoxicity
Elevations of ALT or AST (three or more times the upper limit of normal [ULN]) have been reported in approximately 1% of NSAID-treated patients in clinical trials with NSAIDS. In addition, rare, sometimes fatal, cases of severe hepatic injury, including fulminant hepatitis, liver necrosis, and hepatic failure have been reported.
Elevations of ALT or AST (less than three times ULN) may occur in up to 15% of patients taking NSAIDs including ibuprofen.
Inform patients of the warning signs and symptoms of hepatotoxicity (e.g., nausea, fatigue, lethargy, diarrhea, pruritus, jaundice, right upper quadrant tenderness, and “flulike” symptoms). If clinical signs and symptoms consistent with liver disease develop, or if systemic manifestations occur (e.g., eosinophilia, rash, etc.), discontinue hydrocodone bitartrate and ibuprofen tablets immediately, and perform a clinical evaluation of the patient.
Hypertension

NSAID-containing products, including, can lead to new onset or worsening of pre-existing hypertension, both Hydrocodone Bitartrate and Ibuprofen Tablets of which may contribute to the increased incidence of CV events. Patients taking angiotensin converting enzyme (ACE) inhibitors, thiazide diuretics, or loop diuretics may have impaired response to these therapies when taking NSAIDs (see PRECAUTIONS: Drug Interactions).

Monitor blood pressure (BP) during the initiation of NSAID treatment and throughout the course of therapy.
Heart Failure and Edema
The Coxib and Traditional NSAID Trialists’ Collaboration meta-analysis of randomized controlled trials demonstrated an approximately two-fold increase in hospitalizations for heart failure in COX-2 selective-treated patients and nonselective NSAID-treated patients compared to placebo-treated patients. In a Danish National Registry study of patients with heart failure, NSAID use increased the risk of MI, hospitalization for heart failure, and death.
Additionally, fluid retention and edema have been observed in some patients treated with NSAIDs. Use of hydrocodone bitartrate and ibuprofen tablets may blunt the CV effects of several therapeutic agents used to treat these medical conditions (e.g., diuretics, ACE inhibitors, or angiotensin receptor blockers [ARBs]) (see PRECAUTIONS: Drug Interactions).
Avoid the use of hydrocodone bitartrate and ibuprofen tablets in patients with severe heart failure unless the benefits are expected to outweigh the risk of worsening heart failure. If hydrocodone bitartrate and ibuprofen tablets are used in patients with severe heart failure, monitor patients for signs of worsening heart failure.

Renal Toxicity and Hyperkalemia

Renal Toxicity

Long-term administration of NSAIDs has resulted in renal papillary necrosis and other renal injury.Renal toxicity has also been seen in patients in whom renal prostaglandins have a compensatory role in the maintenance of renal perfusion. In these patients, administration of an NSAID may cause a dose-dependent reduction in prostaglandin formation and, secondarily, in renal blood flow, which may precipitate overt renal decompensation. Patients at greatest risk of this reaction are those with impaired renal function, dehydration, hypovolemia, heart failure, liver dysfunction, those taking diuretics and ACE inhibitors or angiotensin receptor blockers (ARBs), and the elderly. Discontinuation of NSAID therapy was usually followed by recovery to the pretreatment state.

No information is available from controlled clinical studies regarding the use of hydrocodone bitartrate and ibuprofen tablets in patients with advanced renal disease. The renal effects of hydrocodone bitartrate and ibuprofen tablets may hasten the progression of renal dysfunction in patients with pre-existing renal disease.
Correct volume status in dehydrated or hypovolemic patients prior to initiating Hydrocodone Bitartrate and Ibuprofen Tablets. Monitor renal function in patients with renal or hepatic impairment, heart failure, dehydration, or hypovolemia during use of hydrocodone bitartrate and ibuprofen tablets (see PRECAUTIONS: Drug Interactions). Avoid the use of hydrocodone bitartrate and ibuprofen tablets in patients with advanced renal disease unless the benefits are expected to outweigh the risk of worsening renal function. If hydrocodone bitartrate and ibuprofen tablets are used in patients with advanced renal disease, monitor patients for signs of worsening renal function.

Hyperkalemia

Increases in serum potassium concentration, including hyperkalemia, have been reported with use of NSAIDs, even in some patients without renal impairment. In patients with normal renal function, those effects have been attributed to a hyporeninemic-hypoaldosteronism state.

Anaphylactic Reactions

Ibuprofen has been associated with anaphylactic reactions in patients with and without known hypersensitivity to ibuprofen and in patients with aspirin-sensitive asthma (see CONTRAINDICATIONS, WARNINGS: Exacerbation of Asthma Related to Aspirin Sensitivity).
Seek emergency help if an anaphylactic reaction occurs.

Exacerbation of Asthma Related to Aspirin Sensitivity
A subpopulation of patients with asthma may have aspirin-sensitive asthma which may include chronic rhinosinusitis complicated by nasal polyps; severe, potentially fatal bronchospasm; and/or intolerance to aspirin and other NSAIDs. Because cross-reactivity between aspirin and other NSAIDs has been reported in such aspirin-sensitive patients, hydrocodone bitartrate and ibuprofen tablets are contraindicated in patients with this form of aspirin sensitivity (see CONTRAINDICATIONS). When hydrocodone bitartrate and ibuprofen tablets are used in patients with pre-existing asthma (without known aspirin sensitivity), monitor patients for changes in the signs and symptoms of asthma.

Serious Skin Reactions
NSAIDs, including ibuprofen, can cause serious skin adverse reactions such as exfoliative dermatitis, Stevens - Johnson syndrome (SJS), and toxic epidermal necrolysis (TEN), which can be fatal. NSAIDs can also cause fixed drug eruption (FDE). FDE may present as a more severe variant known as generalized bullous fixed drug eruption (GBFDE), which can be life-threatening. These serious events may occur without warning. Inform patients about the signs and symptoms of serious skin reactions, and to discontinue the use of hydrocodone bitartrate and ibuprofen tablets at the first appearance of skin rash or any other sign of hypersensitivity hydrocodone bitartrate and ibuprofen tablets are contraindicated in patients with previous serious skin reactions to NSAIDs (see CONTRAINDICATIONS).

Drug Reaction with Eosinophilia and Systemic Symptoms (DRESS)

Drug Reaction with Eosinophilia and Systemic Symptoms (DRESS) has been reported in patients taking NSAIDs such as Hydrocodone Bitartrate and Ibuprofen Tablets. Some of these events have been fatal or life-threatening. DRESS typically, although not exclusively, presents with fever, rash, lymphadenopathy, and/or facial swelling. Other clinical manifestations may include hepatitis, nephritis, hematological abnormalities, myocarditis, or myositis. Sometimes symptoms of DRESS may resemble an acute viral infection. Eosinophilia is often present. Because this disorder is variable in its presentation, other organ systems not noted here may be involved. It is important to note that early manifestations of hypersensitivity, such as fever or lymphadenopathy, may be present even though rash is not evident. If such signs or symptoms are present, discontinue Hydrocodone Bitartrate and Ibuprofen Tablets and evaluate the patient immediately.

Fetal Toxicity
Premature Closure of Fetal Ductus Arteriosus:
Avoid use of NSAIDs, including Hydrocodone Bitartrate And Ibuprofen Tablets, in pregnant women at about 30 weeks gestation and later. NSAIDs including Hydrocodone Bitartrate And Ibuprofen Tablets, increase the risk of premature closure of the fetal ductus arteriosus at approximately this gestational age.

Oligohydramnios/Neonatal Renal Impairment:
Use of NSAIDs, including Hydrocodone Bitartrate And Ibuprofen Tablets, at about 20 weeks gestation or later in pregnancy may cause fetal renal dysfunction leading to oligohydramnios and, in some cases, neonatal renal impairment. These adverse outcomes are seen, on average, after days to weeks of treatment, although oligohydramnios has been infrequently reported as soon as 48 hours after NSAID initiation.
Oligohydramnios is often, but not always, reversible with treatment discontinuation. Complications of prolonged oligohydramnios may, for example, include limb contractures and delayed lung maturation. In some postmarketing cases of impaired neonatal renal function, invasive procedures such as exchange transfusion or dialysis were required.

If NSAID treatment is necessary between about 20 weeks and 30 weeks gestation, limit Hydrocodone Bitartrate And Ibuprofen Tablets use to the lowest effective dose and shortest duration possible. Consider ultrasound monitoring of amniotic fluid if Hydrocodone Bitartrate And Ibuprofen Tablets treatment extends beyond 48 hours. Discontinue Hydrocodone Bitartrate And Ibuprofen Tablets if oligohydramnios occurs and follow up according to clinical practice (see PRECAUTIONS; Pregnancy).

Hematologic Toxicity

Anemia has occurred in NSAID-treated patients. This may be due to occult or gross blood loss, fluid retention, or an incompletely described effect on erythropoiesis. If a patient treated with hydrocodone bitartrate and ibuprofen tablets have any signs or symptoms of anemia, monitor hemoglobin or hematocrit.

NSAID-containing products, including Hydrocodone Bitartrate and Ibuprofen Tablets, may increase the risk of bleeding events. Co-morbid conditions such as coagulation disorders, concomitant use of warfarin, other anticoagulants, antiplatelet agents (e.g., aspirin), serotonin reuptake inhibitors (SSRIs), and serotonin norepinephrine reuptake inhibitors (SNRIs) may increase this risk. Monitor these patients for signs of bleeding (see PRECAUTIONS: Drug Interactions).

Aseptic Meningitis

Aseptic meningitis with fever and coma has been observed on rare occasions in patients on ibuprofen therapy as found in Hydrocodone Bitartrate and Ibuprofen Tablets. Although it is probably more likely to occur in patients with systemic lupus erythematosus and related connective tissue diseases, it has been reported in patients who do not have an underlying chronic disease. If signs or symptoms of meningitis develop in a patient on Hydrocodone Bitartrate and Ibuprofen Tablets, the possibility of its being related to ibuprofen should be considered

PRECAUTIONS

Masking of Inflammation and Fever
The pharmacological activity of hydrocodone bitartrate and ibuprofen tablets in reducing inflammation, and possibly fever, may diminish the utility of diagnostic signs in detecting infections.
Ophthalmological Effects
Blurred or diminished vision, scotomata, and changes in color vision have been reported with oral ibuprofen. Discontinue ibuprofen if a patient develops such complaints, and refer the patient for an ophthalmologic examination that includes central visual fields and color vision testing.

Information for Patients

Advise the patient to read the FDA-approved patient labeling (Medication Guide) that accompanies each prescription dispensed. Patients, families, or their caregivers should be informed of the following information before initiating therapy with hydrocodone bitartrate and ibuprofen tablets and periodically during the course of ongoing therapy.

1. Storage and Disposal:

Because of the risks associated with accidental ingestion, misuse, and abuse, advise patients to store Hydrocodone Bitartrate and Ibuprofen Tablets securely, out of sight and reach of children, and in a location not accessible by others, including visitors to the home. Inform patients that leaving Hydrocodone Bitartrate and Ibuprofen Tablets unsecured can pose a deadly risk to others in the home. (see WARNINGS, DRUG ABUSE AND DEPENDENCE)

Advise patients and caregivers that when medicines are no longer needed, they should be disposed of promptly. Expired, unwanted, or unused Hydrocodone Bitartrate and Ibuprofen Tablets should be disposed of by flushing the unused medication down the toilet if a drug take-back option is not readily available. Inform patients that they can visit www.fda.gov/drugdisposal for a complete list of medicines recommended for disposal by flushing, as well as additional information on disposal of unused medicines.

2. Addiction, Abuse, and Misuse

Inform patients that the use of Hydrocodone Bitartrate And Ibuprofen Tablets, even when taken as recommended, can result in addiction, abuse, and misuse, which can lead to overdose and death (see WARNINGS: Addiction, Abuse, and Misuse). Instruct patients not to share hydrocodone bitartrate and ibuprofen tablets with others and to take steps to protect hydrocodone bitartrate and ibuprofen tablets from theft or misuse.

3. Life-Threatening Respiratory Depression

Inform patients of the risk of life-threatening respiratory depression, including information that the risk is greatest when starting hydrocodone bitartrate and ibuprofen tablets or when the dosage is increased, and that it can occur even at recommended dosages. Advise patients how to recognize respiratory depression and to seek medical attention if breathing difficulties develop.

Educate patients and caregivers on how to recognize respiratory depression and emphasize the importance of calling 911 or getting emergency medical help right away in the event of a known or suspected overdose (see WARNINGS, Life Threatening Respiratory Depression).

4. Accidental Ingestion

Inform patients that accidental ingestion, especially by children, may result in respiratory depression or death (see WARNINGS: Life-Threatening Respiratory Depression).

5. Interactions with Benzodiazepines and OtherCNS Depressants

Inform patients and caregivers that potentially fatal additive effects may occur if hydrocodone bitartrate and ibuprofen tablets are used with benzodiazepines or other CNS depressants, including alcohol,(e.g., non-benzodiazepine sedative/hypnotics, anxiolytics, tranquilizers, muscle relaxants, general anesthetics, antipsychotics, gabapentinoids [gabapentin or pregabalin], and other opioids) and not to use these concomitantly unless supervised by a healthcare provider (see WARNINGS: Risks from Concomitant Use with Benzodiazepines or Other CNS Depressants, PRECAUTIONS: Drug Interactions).

Patient Access to an Opioid Overdose Reversal Agent for the Emergency Treatment of Opioid Overdose

Inform patients and caregivers about opioid overdose reversal agents (e.g., naloxone, nalmefene). Discuss the importance of having access to an opioid overdose reversal agent, especially if the patient has risk factors for overdose (e.g., concomitant use of CNS depressants, a history of opioid use disorder, or prior opioid overdose) or if there are household members (including children) or other close contacts at risk for accidental ingestion or opioid overdose.

Discuss with the patient the options for obtaining an opioid overdose reversal agent (e.g., prescription, over-the-counter, or as part of a community-based program) [see WARNINGS, DOSAGE AND ADMINISTRATION].
Educate patients and caregivers on how to recognize the signs and symptoms of an overdose.
Explain to patients and caregivers that effects of opioid overdose reversal agents like naloxone and nalmefene are temporary, and that they must call 911 or get emergency medical help right away in all cases of known or suspected opioid overdose, even if an opioid overdose reversal agent is administered (see OVERDOSAGE).
Advise patients and caregivers:
• how to treat with the overdose reversal agent in the event of an opioid overdose
• to tell family and friends about their opioid overdose reversal agent and to keep it in a place where family and friends can access it in an emergency.
• to read the Patient Information (or other educational material) that will come with their opioid overdose reversal agent. Emphasize the importance of doing this before an opioid emergency happens, so the patient and caregiver will know what to do.
Hyperalgesia and Allodynia

Inform patients and caregivers not to increase opioid dosage without first consulting a clinician. Advise patients to seek medical attention if they experience symptoms of hyperalgesia, including worsening pain, increased sensitivity to pain, or new pain [see Warnings; Adverse Reactions].

8. Serotonin Syndrome

Inform patients that opioids could cause a rare but potentially life-threatening condition resulting from concomitant administration of serotonergic drugs. Warn patients of the symptoms of serotonin syndrome and to seek medical attention right away if symptoms develop. Instruct patients to inform their healthcare providers if they are taking, or plan to take serotonergic medications (see PRECAUTIONS: Drug Interactions).

9. MAOI Interaction

Inform patients to avoid taking hydrocodone bitartrate and ibuprofen tablets while using any drugs that inhibit monoamine oxidase. Patients should not start MAOIs while taking hydrocodone bitartrate and ibuprofen tablets (see PRECAUTIONS: Drug Interactions).

10. Important Administration Instructions

Instruct patients how to properly take Hydrocodone Bitartrate and Ibuprofen Tablets. For the short-term (generally less than 10 days) management of acute pain, the recommended dose of hydrocodone bitartrate and ibuprofen tablets are one tablet every 4 to 6 hours, as necessary. Inform patients that the dosage should not exceed 5 tablets in a 24-hour period (see DOSAGE AND ADMINISTRATION).

11. Important Discontinuation Instructions

In order to avoid developing withdrawal symptoms, instruct patients not to discontinue Hydrocodone Bitartrate and Ibuprofen Tablets without first discussing a tapering plan with the prescriber (see DOSAGE AND ADMINISTRATION)

12. Driving or Operating Heavy Machinery

Inform patients that hydrocodone bitartrate and ibuprofen tablets may impair the ability to perform potentially hazardous activities such as driving a car or operating heavy machinery. Advise patients not to perform such tasks until they know how they will react to the medication (see WARNINGS: Risks of Driving and Operating Machinery).

13. Constipation

Advise patients of the potential for severe constipation, including management instructions and when to seek medical attention (see ADVERSE REACTIONS: Clinical Trials Experience).

14. Cardiovascular Thrombotic Events

Advise patients to be alert for the symptoms of cardiovascular thrombotic events, including chest pain, shortness of breath, weakness, or slurring of speech, and to report any of these symptoms to their healthcare provider immediately (see WARNINGS: Cardiovascular Thrombotic Events).

15. Gastrointestinal Bleeding, Ulceration, and Perforation

Advise patients to report symptoms of ulcerations and bleeding, including epigastric pain, dyspepsia, melena, and hematemesis to their healthcare provider. In the setting of concomitant use of low-dose aspirin for cardiac prophylaxis, inform patients of the increased risk for and the signs and symptoms of GI bleeding (see WARNINGS: Gastrointestinal Bleeding, Ulceration, and Perforation).

16. Hepatotoxicity

Inform patients of the warning signs and symptoms of hepatotoxicity (e.g., nausea, fatigue, lethargy, pruritus, diarrhea, jaundice, right upper quadrant tenderness, and "flu-like" symptoms). If these occur, instruct patients to stop hydrocodone bitartrate and ibuprofen tablets and seek immediate medical therapy (see WARNINGS: Hepatotoxicity).

17. Heart Failure and Edema

Advise patients to be alert for the symptoms of congestive heart failure including shortness of breath, unexplained weight gain, or edema and to contact their healthcare provider if such symptoms occur (see WARNINGS: Heart Failure and Edema).

18. Adrenal Insufficiency

Inform patients that opioids could cause adrenal insufficiency, a potentially life-threatening condition. Adrenal insufficiency may present with non-specific symptoms and signs such as nausea, vomiting, anorexia, fatigue, weakness, dizziness, and low blood pressure. Advise patients to seek medical attention if they experience a constellation of these symptoms (see WARNINGS: Adrenal Insufficiency).

19. Hypotension

Inform patients that hydrocodone bitartrate and ibuprofen tablets may cause orthostatic hypotension and syncope. Instruct patients how to recognize symptoms of low blood pressure and how to reduce the risk of serious consequences should hypotension occur (e.g., sit or lie down, carefully rise from a sitting or lying position) (see WARNINGS: Severe Hypotension).

20. Anaphylaxis

Inform patients that anaphylaxis has been reported with ingredients contained in Hydrocodone Bitartrate and Ibuprofen Tablets. Advise patients how to recognize such a reaction and when to seek medical attention (see CONTRAINDICATIONS, WARNINGS: Anaphylactic Reactions).

21. Pregnancy

Neonatal Opioid Withdrawal Syndrome

Inform female patients of reproductive potential that use of hydrocodone bitartrate and ibuprofen tablets for an extended period of time during pregnancy can result in neonatal opioid withdrawal syndrome, which may be life-threatening if not recognized and treated (see Boxed Warning, WARNINGS: Neonatal Opioid Withdrawal Syndrome, PRECAUTIONS: Pregnancy).

Fetal Toxicity

Inform female patients of reproductive potential that hydrocodone bitartrate and ibuprofen tablets can cause fetal harm and to inform the prescriber of a known or suspected pregnancy. Inform pregnant women to avoid use of hydrocodone bitartrate and ibuprofen tablets and other NSAIDs starting at 30 weeks gestation because of the risk of premature closing of the fetal ductus arteriosus

Inform pregnant women to avoid use of Hydrocodone Bitartrate and Ibuprofen Tablets and other NSAIDs starting at 30 weeks gestation because of the risk of the premature closing of the fetal ductus arteriosus. If treatment with Hydrocodone Bitartrate and Ibuprofen Tablets is needed for a pregnant woman between about 20 to 30 weeks gestation, advise her that she may need to be monitored for oligohydramnios, if treatment continues for longer than 48 hours (see WARNINGS; Fetal Toxicity, PRECAUTIONS; Pregnancy).

22. Lactation

Advise nursing mothers to carefully observe infants for increased sleepiness (more than usual), breathing difficulties, or limpness. Instruct nursing mothers to seek immediate medical care if they notice these signs (see PRECAUTIONS: Nursing Mothers).

23. Infertility

Inform patients that use of opioids for an extended period of time may cause reduced fertility. It is not known whether these effects on fertility are reversible [see Adverse Reaction]. Advise female patients of reproductive potential who desire pregnancy that NSAIDs, including Hydrocodone Bitartrate And Ibuprofen Tablets, may be associated with a reversible delay in ovulation (see PRECAUTIONS: Carcinogenicity, Mutagenicity, Impairment of Fertility).

24. Serious Skin Reactions, including DRESS.

Advise patients to stop taking Hydrocodone Bitartrate and Ibuprofen Tablets immediately if they develop any type of rash or fever and to contact their healthcare provider as soon as possible (see Warnings).

25. Avoid Concomitant use of NSAIDs

Inform patients that the concomitant use of hydrocodone bitartrate and ibuprofen tablets with other NSAIDs or salicylates (e.g., diflunisal, salsalate) is not recommended due to the increased risk of gastrointestinal toxicity, and little or no increase in efficacy (see WARNINGS: Gastrointestinal Bleeding, Ulceration, and Perforation, PRECAUTIONS: Drug Interactions). Alert patients that NSAIDs may be present in “over the counter” medications for treatment of colds, fever, or insomnia.

26. Use of NSAIDS and Low-Dose Aspirin

Inform patients not to use low-dose aspirin concomitantly with hydrocodone bitartrate and ibuprofen tablets until they talk to their healthcare provider (see PRECAUTIONS: Drug Interactions).

27. Ophthalmological Effects

Instruct patients to report any signs of blurred vision or other eye symptoms (see PRECAUTIONS: Ophthalmological Effects).

Laboratory Monitoring

Because serious GI bleeding, hepatotoxicity, and renal injury can occur without warning symptoms or signs, consider monitoring patients with a CBC and a chemistry profile periodically (see WARNINGS: Gastrointestinal Bleeding, Ulceration, and Perforation, Renal Toxicity and Hyperkalemia, Hepatotoxicity).

Drug Interactions

Inhibitors of CYP3A4 and CYP2D6

The concomitant use of hydrocodone bitartrate and ibuprofen tablets and CYP3A4 inhibitors, such as macrolide antibiotics (e.g., erythromycin), azole-antifungal agents (e.g. ketoconazole), protease inhibitors (e.g., ritonavir), can increase the plasma concentration of hydrocodone, resulting in increased or prolonged opioid effects. These effects could be more pronounced with concomitant use of hydrocodone bitartrate and ibuprofen tablets and CYP2D6 and CYP3A4 inhibitors, particularly when an inhibitor is added after a stable dose of hydrocodone bitartrate and ibuprofen tablets are achieved (see WARNINGS: Risks of Concomitant Use or Discontinuation of Cytochrome P450 3A4 Inhibitors and Inducers).

After stopping a CYP3A4 inhibitor, as the effects of the inhibitor decline, the hydrocodone plasma concentration will decrease (seeCLINICAL PHARMACOLOGY: Pharmacokinetics), resulting in decreased opioid efficacy or a withdrawal syndrome in patients who had developed physical dependence to Hydrocodone Bitartrate and Ibuprofen Tablets.

If concomitant use is necessary, consider dosage reduction of hydrocodone bitartrate and ibuprofen tablets until stable drug effects are achieved. Evaluate patients at frequent intervals for respiratory depression and sedation. If a CYP3A4 inhibitor is discontinued, consider a dosage increase of hydrocodone bitartrate and ibuprofen tablets until stable drug effects are achieved. Evaluate for signs of opioid withdrawal.

CYP3A4 Inducers

The concomitant use of hydrocodone bitartrate and ibuprofen tablets and CYP3A4 inducers, such as rifampin, carbamazepine, and phenytoin, can decrease the plasma concentration of hydrocodone (see CLINICAL PHARMACOLOGY: Pharmacokinetics), resulting in decreased efficacy or onset of a withdrawal syndrome in patients who have developed physical dependence to hydrocodone (see WARNINGS: Withdrawal).

After stopping a CYP3A4 inducer, as the effects of the inducer decline, the hydrocodone plasma concentration will increase (see CLINICAL PHARMACOLOGY: Pharmacokinetics), which could increase or prolong both the therapeutic effects and adverse reactions, and may cause serious respiratory depression.

If concomitant use is necessary, consider a dosage increase of hydrocodone bitartrate and ibuprofen tablets until stable drug effects are achieved. Evaluate for signs of opioid withdrawal. If a CYP3A4 inducer is discontinued, consider hydrocodone bitartrate and ibuprofen tablets dosage reduction and evaluate patients at frequent intervals for signs of respiratory depression and sedation.

Benzodiazepines and Other Central Nervous System (CNS) Depressants

Due to additive pharmacologic effect, the concomitant use of benzodiazepines and other CNS depressants, such as benzodiazepines and other sedative hypnotics, anxiolytics, and tranquilizers, muscle relaxants, general anesthetics, antipsychotics, gabapentinoids (gabapentin or pregabalin) and other opioids, including alcohol, can increase the risk of hypotension, respiratory depression, profound sedation, coma, and death.

Reserve concomitant prescribing of these drugs for use in patients for whom alternative treatment options are inadequate. Limit dosages and durations to the minimum required. Inform patients and caregivers of this potential interaction, educate them on the signs and symptoms of respiratory depression (including sedation). If concomitant use is warranted, consider recommending or prescribing an opioid overdose reversal agent [see WARNINGS, DOSAGE AND ADMINISTRATION].

Serotonergic Drugs

The concomitant use of opioids with other drugs that affect the serotonergic neurotransmitter system, such as selective serotonin reuptake inhibitors (SSRIs), serotonin and norepinephrine reuptake inhibitors (SNRIs), tricyclic antidepressants (TCAs), triptans, 5-HT3 receptor antagonists, drugs that effect the serotonin neurotransmitter system (e.g., mirtazapine, trazodone, tramadol), certain muscle relaxants (i.e., cyclobenzaprine,metaxalone), and monoamine oxidase (MAO) inhibitors (those intended to treat psychiatric disorders and also others, such as linezolid and intravenous methylene blue), has resulted in serotonin syndrome (see PRECAUTIONS: Information for Patients).

If concomitant use is warranted, frequently evaluate the patient, particularly during treatment initiation and dose adjustment. Discontinue hydrocodone bitartrate and ibuprofen tablets if serotonin syndrome is suspected.

Monoamine Oxidase Inhibitors (MAOIs)

MAOI interactions with opioids may manifest as serotonin syndrome or opioid toxicity (e.g., respiratory depression, coma).

If urgent use of an opioid is necessary with MAOIs such as phenelzine, tranylcypromine, linezolid, use test doses and frequent titration of small doses to treat pain while closely monitoring blood pressure and signs and symptoms of CNS and respiratory depression.

The use of hydrocodone bitartrate and ibuprofen tablets are not recommended for patients taking MAOIs or within 14 days of stopping such treatment.

Mixed Agonist/Antagonist and Partial Agonist Opioid Analgesics

Agonist/antagonist analgesics such as pentazocine, nalbuphine, butorphanol and buprenorphine may reduce the analgesic effect of hydrocodone bitartrate and ibuprofen tablets and/or precipitate withdrawal symptoms in these patients.

Avoid concomitant use of these drugs.
Muscle Relaxants

Hydrocodone Bitartrate and Ibuprofen Tablets may enhance the neuromuscular blocking action of skeletal muscle relaxants and produce an increased degree of respiratory depression.

Because respiratory depression may be greater than otherwise expected, decrease the dosage of hydrocodone bitartrate and ibuprofen tablets and/or the muscle relaxant as necessary. Due to the risk of respiratory depression with concomitant use of skeletal muscle relaxants and opioids, consider recommending or prescribing an opioid overdose reversal agent (see WARNINGS, DOSAGE AND ADMINISTRATION). Examples: Cyclobenzaprine, metaxalone.

Anticholinergics

The concomitant use of anticholinergic drugs may increase risk of urinary retention and/or severe constipation, which may lead to paralytic ileus.

Evaluate patients for signs of urinary retention or reduced gastric motility when hydrocodone bitartrate and ibuprofen tablets are used concomitantly with anticholinergic drugs.

Drugs That Interfere With Hemostasis

Ibuprofen and anticoagulants such as warfarin have a synergistic effect on bleeding. The concomitant use of ibuprofen and anticoagulants have an increased risk of serious bleeding compared to the use of either drug alone.
Serotonin release by platelets plays an important role in hemostasis. Case-control and cohort epidemiological studies showed that concomitant use of drugs that interfere with serotonin reuptake and an NSAID may potentiate the risk of bleeding more than an NSAID alone.

Monitor patients with concomitant use of hydrocodone bitartrate and ibuprofen tablets with anticoagulants (e.g., warfarin), antiplatelet agents (e.g., aspirin), SSRIs, and SNRIs for signs of bleeding (see WARNINGS: Hematologic Toxicity).

Aspirin

Pharmacodynamic studies have demonstrated interference with the antiplatelet activity of aspirin when ibuprofen 400 mg, given three times daily, is administered with enteric coated low-dose aspirin. The interaction exists even following a once-daily regimen of ibuprofen 400 mg, particularly when ibuprofen is dosed prior to aspirin. The interaction is alleviated if immediate-release low-dose aspirin is dosed at least 2 hours prior to a once daily regimen of ibuprofen; however, this finding cannot be extended to enteric-coated low-dose aspirin [see Clinical Pharmacology/Pharmacodynamics].

Because there may be an increased risk of cardiovascular events due to the interference of ibuprofen with the antiplatelet effect of aspirin, for patients taking low-dose aspirin for cardioprotection who require analgesics, consider use of an NSAID that does not interfere with the antiplatelet effect of aspirin, or non-NSAID analgesics, where appropriate.

Controlled clinical studies showed that the concomitant use of NSAIDs and analgesic doses of aspirin does not produce any greater therapeutic effect than the use of NSAIDs alone. In a clinical study, the concomitant use of an NSAID and aspirin was associated with a significantly increased incidence of GI adverse reactions as compared to use of the NSAID alone (see WARNINGS: Gastrointestinal Bleeding, Ulceration, and Perforation).

Concomitant use of hydrocodone bitartrate and ibuprofen tablets and analgesic doses of aspirin is not generally recommended because of the increased risk of bleeding (see WARNINGS: Hematologic Toxicity).

ACE-Inhibitors, Angiotensin Receptor Blockers, and Beta-blockers

NSAIDs may diminish the antihypertensive effect of angiotensin converting enzyme (ACE) inhibitors, angiotensin receptor blockers (ARBs), or beta-blockers (including propranolol).

During concomitant use of hydrocodone bitartrate and ibuprofen tablets and ACE-inhibitors, ARBs, or beta-blockers, monitor blood pressure to ensure that the desired blood pressure is obtained.

In patients who are elderly, volume-depleted (including those on diuretic therapy), or have renal impairment, co-administration of an NSAID with ACE inhibitors or ARBs may result in deterioration of renal function, including possible acute renal failure. Evaluate for signs of worsening renal function (see WARNINGS: Renal Toxicity and Hyperkalemia). These effects are usually reversible.

When these drugs are administered concomitantly, patients should be adequately hydrated. Assess renal function at the beginning of the concomitant treatment and periodically thereafter.

Diuretics

Clinical studies, as well as post-marketing observations, showed that NSAIDs reduced the natriuretic effect of loop diuretics (e.g., furosemide) and thiazide diuretics in some patients. This effect has been attributed to the NSAID inhibition of renal prostaglandin synthesis.

During concomitant use of hydrocodone bitartrate and ibuprofen tablets with diuretics, observe patients for signs of worsening renal function, in addition to assuring diuretic efficacy including antihypertensive effects (see WARNINGS: Renal Toxicity and Hyperkalemia).

Digoxin

The concomitant use of ibuprofen with digoxin has been reported to increase the serum concentration and prolong the half-life of digoxin.

During concomitant use of hydrocodone bitartrate and ibuprofen tablets and digoxin, monitor serum digoxin levels.

Lithium

NSAIDs have produced elevations in plasma lithium concentration and reductions in renal lithium clearance. The mean minimum lithium concentration increased 15%, and the renal clearance decreased by approximately 20%. This effect has been attributed to NSAID inhibition of renal prostaglandin synthesis.

During concomitant use of hydrocodone bitartrate and ibuprofen tablets and lithium, evaluate patients for signs of lithium toxicity.

Methotrexate

Concomitant use of NSAIDs and methotrexate may increase the risk for methotrexate toxicity (e.g., neutropenia, thrombocytopenia, renal dysfunction).

During concomitant use of hydrocodone bitartrate and ibuprofen tablets and methotrexate, evaluate patients for methotrexate toxicity.

Cyclosporine

Concomitant use of hydrocodone bitartrate and ibuprofen tablets and cyclosporine may increase cyclosporine’s nephrotoxicity.

During concomitant use of hydrocodone bitartrate and ibuprofen tablets and cyclosporine, evaluate patients for signs of worsening renal function.

NSAIDs and Salicylates

Concomitant use of ibuprofen with other NSAIDs or salicylates (e.g., diflunisal, salsalate) increases the risk of GI toxicity, with little or no increase in efficacy (see WARNINGS: Gastrointestinal Bleeding, Ulceration, and Perforation).

The concomitant use of ibuprofen with other NSAIDs or salicylates is not recommended.
Pemetrexed
Concomitant use of hydrocodone bitartrate and ibuprofen tablets and Pemetrexed may increase the risk of Pemetrexed associated myelosuppression, renal, and GI toxicity (see the Pemetrexed prescribing information).

During concomitant use of hydrocodone bitartrate and ibuprofen tablets and Pemetrexed, in patients with renal impairment whose creatinine clearance ranges from 45 to 79 mL/min, monitor for myelosuppression, renal and GI toxicity.

NSAIDs with short elimination half-lives (e.g., diclofenac, indomethacin) should be avoided for a period of two days before, the day of, and two days following administration of Pemetrexed.

In the absence of data regarding potential interaction between Pemetrexed and NSAIDs with longer half-lives (e.g., meloxicam, nabumetone), patients taking these NSAIDs should interrupt dosing for at least five days before, the day of, and two days following Pemetrexed administration.

Carcinogenicity, Mutagenicity, Impairment of Fertility

Carcinogenesis

Long-term animal studies to evaluate the carcinogenic potential of the combination of hydrocodone and ibuprofen, ibuprofen alone, or hydrocodone alone have not been conducted.

Mutagenesis

The mutagenic potential of the combination of hydrocodone and ibuprofen or hydrocodone alone has not been investigated.

In published studies, ibuprofen was not mutagenic in the in vitro bacterial reverse mutation assay (Ames assay).
Impairment of Fertility
Animal studies evaluating the impact of the combination of hydrocodone and ibuprofen or hydrocodone alone on fertility have not been conducted.

In a published study, dietary administration of ibuprofen to male and female rats 8-weeks prior to and during mating at dose levels of 20 mg/kg (0.2-times the MRHD of 1000 mg ibuprofen based on body surface area comparison) did not impact male or female fertility or litter size.

In other studies, adult mice were administered ibuprofen intraperitoneally at a dose of 5.6 mg/kg/day (0.03-times the MRHD based on body surface area comparison) for 35 or 60 days in males and 35 days in females. There was no effect on sperm motility or viability in males but decreased ovulation was reported in females.

Based on the mechanism of action, the use of prostaglandin-mediated NSAIDs, including ibuprofen, may delay or prevent rupture of ovarian follicles, which has been associated with reversible infertility in some women. Small studies in women treated with NSAIDs have also shown a reversible delay in ovulation. Consider withdrawal of NSAID-containing products, including Hydrocodone Bitartrate and Ibuprofen Tablets, in women who have difficulties conceiving or who are undergoing investigation of infertility.

Use of opioids for an extended period of time may cause reduced fertility in females and males of reproductive potential. It is not known whether these effects on fertility are reversible (see ADVERSE REACTIONS: Postmarketing Experience).

Pregnancy

Risk Summary

Use of NSAIDs, including Hydrocodone Bitartrate and Ibuprofen Tablets, can cause premature closure of the fetal ductus arteriosus and fetal renal dysfunction leading to oligohydramnios and, in some cases, neonatal renal impairment. Because of these risks, limit dose and duration of Hydrocodone Bitartrate and Ibuprofen Tablets use between about 20 and 30 weeks of gestation, and avoid Hydrocodone Bitartrate and Ibuprofen Tablets use at about 30 weeks of gestation and later in pregnancy (see WARNINGS; Fetal Toxicity).

Premature Closure of Fetal Ductus Arteriosus
Use of NSAIDs, including Hydrocodone Bitartrate and Ibuprofen Tablets, at about 30 weeks gestation or later in pregnancy increases the risk of premature closure of the fetal ductus arteriosus.

Oligohydramnios/Neonatal Renal Impairment
Use of NSAIDs at about 20 weeks gestation or later in pregnancy has been associated with cases of fetal renal dysfunction leading to oligohydramnios, and in some cases, neonatal renal impairment.

Data from observational studies regarding other potential embryofetal risks of NSAID use in women in the first or second trimesters of pregnancy are inconclusive. In animal reproduction studies, an increase in the percentage of litters and fetuses with any major abnormality and an increase in the number of litters and fetuses with one or more nonossified metacarpals was observed when the combination of hydrocodone and ibuprofen was administered orally to pregnant rabbits during organogenesis at 1.8 times the maximum daily dose. There are no animal reproductive and developmental toxicology studies with hydrocodone alone. In published animal reproduction studies testing ibuprofen alone, there were no clear developmental effects at doses up to 1.2 times the maximum recommended human dose (MRHD) in the rabbit and 1.8 times in the MRHD rat when dosed throughout gestation. In contrast, an increase in membranous ventricular septal defects was reported in rats treated on Gestation Days 9 & 10 with 3 times the MRHD. Based on animal data, prostaglandins have been shown to have an important role in endometrial vascular permeability, blastocyst implantation, and decidualization. In animal studies, administration of prostaglandin synthesis inhibitors such as ibuprofen, resulted in increased pre- and post-implantation loss. Prostaglandins also have been shown to have an important role in fetal kidney development. In published animal studies, prostaglandin synthesis inhibitors have been reported to impair kidney development when administered at clinically relevant doses.
The estimated background risk of major birth defects and miscarriage for the indicated population(s) is unknown. All pregnancies have a background risk of birth defect, loss, or other adverse outcomes. In the U.S. general population, the estimated background risk of major birth defects and miscarriage in clinically recognized pregnancies is 2-4% and 15-20%, respectively.

Clinical Considerations

Fetal/Neonatal Adverse Reactions

Use of opioid analgesics for an extended period of time during pregnancy for medical or nonmedical purposes can result in physical dependence in the neonate and neonatal opioid withdrawal syndrome shortly after birth.

Neonatal opioid withdrawal syndrome presents as irritability, hyperactivity and abnormal sleep pattern, high-pitched cry, tremor, vomiting, diarrhea, and failure to gain weight. The onset, duration, and severity of neonatal opioid withdrawal syndrome vary based on the specific opioid used, duration of use, timing and amount of last maternal use, and rate of elimination of the drug by the newborn. Observe newborns for symptoms of neonatal opioid withdrawal syndrome and manage accordingly (see WARNINGS: Neonatal Opioid Withdrawal Syndrome).

Premature Closure of Fetal Ductus Arteriosus:
Avoid use of NSAIDs in women at about 30 weeks gestation and later in pregnancy, because NSAIDs, including Hydrocodone Bitartrate and Ibuprofen Tablets, can cause premature closure of the fetal ductus arteriosus (see WARNINGS; Fetal Toxicity).

Oligohydramnios/Neonatal Renal Impairment
If an NSAID is necessary at about 20 weeks gestation or later in pregnancy, limit the use to the lowest effective dose and shortest duration possible. If Hydrocodone Bitartrate and Ibuprofen Tablets treatment extends beyond 48 hours, consider monitoring with ultrasound for oligohydramnios. If oligohydramnios occurs, discontinue Hydrocodone Bitartrate and Ibuprofen Tablets and follow up according to clinical practice (see WARNINGS; Fetal Toxicity).
Labor and Delivery

Opioids cross the placenta and may produce respiratory depression and psycho-physiologic effects in neonates. An opioid overdose reversal agent, such as naloxone, must be available for reversal of opioid-induced respiratory depression in the neonate. Monitor neonates exposed to opioid analgesics during labor for signs of excess sedation and respiratory depression.

There are no studies on the effects of hydrocodone bitartrate and ibuprofen tablets during labor or delivery. In animal studies, NSAIDs, including ibuprofen, inhibit prostaglandin synthesis, cause delayed parturition, and increase the incidence of stillbirth.

Hydrocodone bitartrate and ibuprofen tablets are not recommended for use in women during and immediately prior to labor, when use of shorter-acting analgesics or other analgesic techniques are more appropriate. Opioid analgesics, including Hydrocodone Bitartrate and Ibuprofen Tablets, can prolong labor through actions that temporarily reduce the strength, duration, and frequency of uterine contractions. However, this effect is not consistent and may be offset by an increased rate of cervical dilatation, which tends to shorten labor. Monitor neonates exposed to opioid analgesics during labor for signs of excess sedation and respiratory depression.
Data
Human Data

Premature Closure of Fetal Ductus Arteriosus:
Published literature reports that the use of NSAIDs at about 30 weeks of gestation and later in pregnancy may cause premature closure of the fetal ductus arteriosus.

Oligohydramnios/Neonatal Renal Impairment:
Published studies and postmarketing reports describe maternal NSAID use at about 20 weeks gestation or later in pregnancy associated with fetal renal dysfunction leading to oligohydramnios, and in some cases, neonatal renal impairment. These adverse outcomes are seen, on average, after days to weeks of treatment, although oligohydramnios has been infrequently reported as soon as 48 hours after NSAID initiation. In many cases, but not all, the decrease in amniotic fluid was transient and reversible with cessation of the drug. There have been a limited number of case reports of maternal NSAID use and neonatal renal dysfunction without oligohydramnios, some of which were irreversible. Some cases of neonatal renal dysfunction required treatment with invasive procedures, such as exchange transfusion or dialysis.

Methodological limitations of these postmarketing studies and reports include lack of a control group; limited information regarding dose, duration, and timing of drug exposure; and concomitant use of other medications. These limitations preclude establishing a reliable estimate of the risk of adverse fetal and neonatal outcomes with maternal NSAID use. Because the published safety data on neonatal outcomes involved mostly preterm infants, the generalizability of certain reported risks to the full-term infant exposed to NSAIDs through maternal use is uncertain.

Animal Data

Pregnant rabbits were treated with 10, 33, or 95 mg/kg of 1:27 ratio of hydrocodone:ibuprofen (the high dose is 1.8 times the maximum daily dose of both compounds based on surface area) from Gestation Day 5 to 18. The dose of 95 mg/kg of the combination, which also produced maternal toxicity (44% decrease in body weight gain compared to control), resulted in an increase in the percentage of litters and fetuses with any major abnormality and an increase in the number of litters and fetuses with one or more nonossified metacarpals (a minor abnormality).

Pregnant rats were treated with 50, 100, or 166 mg/kg of a 1:27 ratio of hydrocodone:ibuprofen (the high dose is 1.6 times the maximum daily dose of both compounds based on body surface area) from Gestation Day 5 to 15. No reproductive toxicity was noted despite the presence of maternal toxicity in the 100 and 166 mg/kg groups (21% and 60% decrease in body weight gain compared to control).

In a published study, female rabbits given 7.5, 20, or 60 mg/kg ibuprofen (0.15, 0.39, or 1.2 times the maximum recommended human daily dose of 1000 mg of ibuprofen based on body surface area) from Gestation Days 1 to 29, no clear treatment-related adverse developmental effects were noted. This dose was associated with significant maternal toxicity (stomach ulcers, gastric lesions). In the same publication, female rats were administered 7.5, 20, 60, 180 mg/kg ibuprofen (0.07, 0.2, 0.6, 1.8 times the maximum daily dose) did not result in clear adverse developmental effects. Maternal toxicity (gastrointestinal lesions) was noted at 20 mg/kg and above.

In a published study, rats were orally dosed with 300 mg/kg ibuprofen (3 times the maximum human daily dose of 1000 mg based on body surface area) during Gestation Days 9 and 10 (critical time points for heart development in rats). Ibuprofen treatment resulted in an increase in the incidence of membranous ventricular septal defects. This dose was associated with significant maternal toxicity including gastrointestinal toxicity (1 out of 20 animals). In the same study/publication rabbits were dosed on Gestation Day 9, 10 and 11 with 500 mg/kg (9.7 times the maximum human daily dose), and only one incidence each of a membranous ventricular septal defect and gastroschisis was noted in the rabbit fetuses. This dose was also associated with maternal toxicity.

Nursing Mothers

Risk Summary

Hydrocodone is present in human milk. A published lactation study reports variable concentrations of hydrocodone and hydromorphone (an active metabolite) in breast milk with administration of immediate-release hydrocodone to nursing mothers in the early post-partum period. This lactation study did not assess breastfed infants for potential adverse drug reactions.

Limited published literature reports that, following oral administration, ibuprofen is present in human milk at relative infant doses of 0.06% to 0.6% of the maternal weight-adjusted daily dose.

Lactation studies have not been conducted with Hydrocodone Bitartrate and Ibuprofen Tablets, and no information is available on the effects of the drug on the breastfed infant or the effects of the drug on milk production.

The developmental and health benefits of breastfeeding should be considered along with the mother’s clinical need for hydrocodone bitartrate and ibuprofen tablets and any potential adverse effects on the breastfed infant from hydrocodone bitartrate and ibuprofen tablets or from the underlying maternal condition.

Clinical Considerations

Monitor infants exposed to hydrocodone bitartrate and ibuprofen tablets through breast milk for excess sedation and respiratory depression. Withdrawal symptoms can occur in breastfed infants when maternal administration of hydrocodone is stopped, or when breastfeeding is stopped

Pediatric Use

The safety and effectiveness of hydrocodone bitartrate and ibuprofen tablets in pediatric patients below the age of 16 have not been established.

Geriatric Use

In controlled clinical trials there was no difference in tolerability between patients < 65 years of age and those ≥ 65, apart from an increased tendency of the elderly to develop constipation. However, elderly patients are at greater risk for NSAID-associated serious cardiovascular, gastrointestinal, and renal adverse reactions as well as possible increased risk of respiratory depression with opioids. In general, use caution when selecting a dosage for an elderly patient, usually starting at the low end of the dosing range, reflecting the greater frequency of decreased hepatic, renal, or cardiac function and of concomitant disease or other drug therapy (see WARNINGS: Cardiovascular Thrombotic Events, Gastrointestinal Bleeding, Ulceration, and Perforation, Renal Toxicity and Hyperkalemia).

Respiratory depression is the chief risk for elderly patients treated with opioids, and has occurred after large initial doses were administered to patients who were not opioid-tolerant or when opioids were co-administered with other agents that depress respiration. Titrate the dosage of hydrocodone bitartrate and ibuprofen tablets slowly in geriatric patients and frequently reevaluate the patient for signs of central nervous system and respiratory depression (see WARNINGS).

Both hydrocodone and ibuprofen are known to be substantially excreted by the kidney, and the risk of adverse reactions to this drug may be greater in patients with impaired renal function. Because elderly patients are more likely to have decreased renal function, care should be taken in dose selection, and it may be useful to regularly evaluate renal function.

Hepatic Impairment

Patients with hepatic impairment may have higher hydrocodone plasma concentrations than those with normal function. In patients with severe hepatic impairment, use a low initial dose. Monitor these patients closely for adverse events such as respiratory depression, sedation, and hypotension.

Renal Impairment

Patients with renal impairment may have higher hydrocodone plasma concentrations than those with normal function. Use a low initial dose in patients with renal impairment and monitor closely for adverse events such as respiratory depression, sedation, and hypotension.

ADVERSE REACTIONS

The following adverse reactions are described below and elsewhere in the labeling including the

WARNINGS section.

- Addiction, Abuse, and Misuse
- Life-Threatening Respiratory Depression
- Neonatal Opioid Withdrawal Syndrome
- Interactions with Cytochrome P450 3A4 Inhibitors and Inducers
- Interactions with Benzodiazepines or Other CNS Depressants
- Adrenal Insufficiency
- Severe Hypotension
- Seizures
- Withdrawal
- Cardiovascular Thrombotic Events
- Gastrointestinal Bleeding, Ulceration, and Perforation
- Hepatotoxicity
- Hypertension
- Heart Failure and Edema
- Renal Toxicity and Hyperkalemia
- Anaphylactic Reactions
- Exacerbation of Asthma Related to Aspirin Sensitivity
- Serious Skin Reactions
- Premature Closure of Fetal Ductus Arteriosus
- Hematologic Toxicity
- Aseptic Meningitis
- Opioid-Induced Hyperalgesia and Allodynia [See Warnings]

Clinical Trials Experience

Because clinical trials are conducted under widely varying conditions, adverse reaction rates observed in the clinical trials of a drug cannot be directly compared to rates in the clinical trials of another drug and may not reflect the rates observed in practice.

Hydrocodone bitartrate and ibuprofen tablets were administered to approximately 300 pain patients in a safety study that employed dosages and a duration of treatment sufficient to encompass the recommended usage (see DOSAGE AND ADMINISTRATION). Adverse event rates generally increased with increasing daily dose. The event rates reported below are from approximately 150 patients who were in a group that received one tablet of hydrocodone bitartrate and ibuprofen tablets an average of three to four times daily. The overall incidence rates of adverse experiences in the trials were fairly similar for this patient group and those who received the comparison treatment, acetaminophen 600 mg with codeine 60 mg.

The following lists adverse events that occurred with an incidence of 1% or greater in clinical trials of Hydrocodone Bitartrate and Ibuprofen Tablets, without regard to the causal relationship of the events to the drug. To distinguish different rates of occurrence in clinical studies, the adverse events are listed as follows:

name of adverse event = less than 3%

adverse events marked with an asterisk * = 3% to 9%

adverse event rates over 9% are in parentheses.

Body as a Whole

Abdominal pain*; Asthenia*; Fever; Flu syndrome; Headache (27%); Infection*; Pain.

Cardiovascular

Palpitations; Vasodilation.

Central Nervous System

Anxiety*; Confusion; Dizziness (14%); Hypertonia; Insomnia*; Nervousness*; Paresthesia;

Somnolence (22%); Thinking abnormalities.

Digestive

Anorexia; Constipation (22%); Diarrhea*; Dry mouth*; Dyspepsia (12%); Flatulence*; Gastritis;

Melena; Mouth ulcers; Nausea (21%); Thirst; Vomiting*.

Metabolic and Nutritional Disorders

Edema*.

Respiratory

Dyspnea; Hiccups; Pharyngitis; Rhinitis.

Skin and Appendages

Pruritus*; Sweating*.

Special Senses

Tinnitus.

Urogenital

Urinary frequency.

Incidence less than 1%

Body as a Whole

Allergic reaction.

Cardiovascular

Arrhythmia; Hypotension; Tachycardia.

Central Nervous System

Agitation; Abnormal dreams; Decreased libido; Depression; Euphoria; Mood changes; Neuralgia; Slurred speech; Tremor, Vertigo.

Digestive

Chalky stool; "Clenching teeth"; Dysphagia; Esophageal spasm; Esophagitis; Gastroenteritis; Glossitis; Liver enzyme elevation.

Metabolic and Nutritional

Weight decrease.

Musculoskeletal

Arthralgia; Myalgia.

Respiratory

Asthma; Bronchitis; Hoarseness; Increased cough; Pulmonary congestion; Pneumonia; Shallow breathing; Sinusitis.

Skin and Appendages

Rash; Urticaria.

Special Senses

Altered vision; Bad taste; Dry eyes.

Urogenital

Cystitis; Glycosuria; Impotence; Urinary incontinence; Urinary retention.

Post marketing Experience

The following adverse reactions have been identified during post approval use of hydrocodone. Because these reactions are reported voluntarily from a population of uncertain size, it is not always possible to reliably estimate their frequency or establish a causal relationship to drug exposure.

Serotonin syndrome: Cases of serotonin syndrome, a potentially life-threatening condition, have been reported during concomitant use of opioids with serotonergic drugs.

Adrenal insufficiency: Cases of adrenal insufficiency have been reported with opioid use, more often following greater than one month of use.

Anaphylaxis: Anaphylaxis has been reported with ingredients contained in Hydrocodone Bitartrate and Ibuprofen Tablets.

Androgen deficiency: Cases of androgen deficiency have occurred with chronic use of opioids for an extended period of time.
Hyperalgesia and Allodynia: Cases of hyperalgesia and allodynia have been reported with opioid therapy of any duration [see Warnings]
Hypoglycemia: Cases of hypoglycemia have been reported in patients taking opioids. Most reports were in patients with at least one predisposing risk factor (e.g., diabetes).
Skin and Appendages: exfoliative dermatitis, Stevens-Johnson Syndrome (SJS), toxic epidermal necrolysis (TEN), and fixed drug eruption (FDE).

Opioid-induced esophageal dysfunction (OIED): Cases of OIED have been reported in patients taking opioids and may occur more frequently in patients taking higher doses of opioids, and/or in patients taking opioids longer term [see WARNINGS].
Adverse Reactions from Observational Studies
A prospective, observational cohort study estimated the risks of addiction, abuse, and misuse in patients initiating long-term use of Schedule II opioid analgesics between 2017 and 2021. Study participant included in one or more analyses had been enrolled in selected insurance plans or health systems for at least one year, were free of at least one outcome at baseline, completed a minimum number of follow-up assessments, and either: 1) filled multiple extended-release/long-acting opioid analgesic prescriptions during a 90 day period (n=978); or 2) filled any Schedule II opioid analgesic prescriptions covering at least 70 of 90 days (n=1,244). Those included also had no dispensing of the qualifying opioids in the previous 6 months.
Over 12 months:
• approximately 1% to 6% of participants across the two cohorts newly met criteria for addiction, as assessed with two validated interview-based measures of moderate-to-severe opioid use disorder based on
Diagnostic and Statistical Manual of Mental Disorders, Fifth Edition (DSM-5) criteria, and
• approximately 9% and 22% of participants across the two cohorts newly met criteria for prescription opioid abuse and misuse [defined in DRUG ABUSE AND DEPENDENCE], respectively, as measured with a validated self-reported instrument.
A retrospective, observational cohort study estimated the risk of opioid-involved overdose or opioid overdose-related death in patients with new long-term use of Schedule II opioid analgesics from 2006 through 2016 (n=220,249). Included patients had been enrolled in either one of two commercial insurance programs, one managed care program, or one Medicaid program for at least 9 months. New long-term use was defined as having Schedule II opioid analgesic prescriptions covering at least 70 days’ supply over the 3 months prior to study entry and none during the preceding 6 months. Patients were excluded if they had an opioid-involved overdose in the 9 months prior to study entry. Overdose was measured using a validated medical code-based algorithm with linkage to the National Death Index database. The 5-year cumulative incidence estimates for opioid-involved overdose or opioid overdose-related death ranged from approximately 1.5% to 4% across study sites, counting only the first event during follow-up. Approximately 17% of first opioid overdoses observed over the entire study period (5-11 years, depending on the study site) were fatal. Higher baseline opioid dose was the strongest and most consistent predictor of opioid-involved overdose or opioid overdose-related death. Study exclusion criteria may have selected patients at lower risk of overdose, and substantial loss to follow-up (approximately 80%) also may have biased estimates.
The risk estimates from the studies described above may not be generalizable to all patients receiving opioid analgesics, such as those with exposures shorter or longer than the duration evaluated in the studies.

DRUG ABUSE AND DEPENDENCE

CONTROLLED SUBSTANCE

Hydrocodone bitartrate and ibuprofen tablets contains hydrocodone, a Schedule II controlled substance.

Abuse

Hydrocodone bitartrate and ibuprofen tablets contain hydrocodone, a substance with high potential for misuse and abuse, which can lead to the development of substance use disorder, including addiction [see Warnings].

Misuse is the intentional use, for therapeutic purposes, of a drug by an individual in a way other than prescribed by a healthcare provider or for whom it was not prescribed.

Abuse is the intentional, non-therapeutic use of a drug, even once, for its desirable psychological or physiological effects.

Drug addiction is a cluster of behavioral, cognitive, and physiological phenomena that may include a strong desire to take the drug, difficulties in controlling drug use (e.g., continuing drug use despite harmful consequences, giving a higher priority to drug use than other activities and obligations), and possible tolerance or physical dependence.

Misuse and abuse of Hydrocodone bitartrate and ibuprofen tablets increases risk of overdose, which may lead to central nervous system and respiratory depression, hypotension, seizures, and death. The risk is increased with concurrent abuse of Hydrocodone bitartrate and ibuprofen tablets with alcohol and other CNS depressants. Abuse of and addiction to opioids in some individuals may not be accompanied by concurrent tolerance and symptoms of physical dependence. In addition, abuse of opioids can occur in the absence of addiction.
All patients treated with opioids require careful and frequent reevaluation for signs of misuse, abuse, and addiction, because use of opioid analgesic products carries the risk of addiction even under appropriate medical use.
Patients at high risk of Hydrocodone bitartrate and ibuprofen tablets abuse include those with a history of prolonged use of any opioid, including products containing hydrocodone, those with a history of drug or alcohol abuse, or those who use Hydrocodone bitartrate and ibuprofen tablets in combination with other abused drugs.
“Drug-seeking” behavior is very common in persons with substance use disorders. Drug-seeking tactics include emergency calls or visits near the end of office hours, refusal to undergo appropriate examination, testing, or referral, repeated “loss” of prescriptions, tampering with prescriptions, and reluctance to provide prior medical records or contact information for other treating healthcare provider(s). “Doctor shopping” (visiting multiple prescribers to obtain additional prescriptions) is common among people who abuse drugs and people with substance use disorder. Preoccupation with achieving adequate pain relief can be appropriate behavior in a patient with inadequate pain control.
Hydrocodone bitartrate and ibuprofen tablets, like other opioids, can be diverted for nonmedical use into illicit channels of distribution. Careful record-keeping of prescribing information, including quantity, frequency, and renewal requests, as required by state and federal law, is strongly advised.

Proper assessment of the patient, proper prescribing practices, periodic reevaluation of therapy, and proper dispensing and storage are appropriate measures that help to limit abuse of opioid drugs.

Risks Specific to Abuse of Hydrocodone Bitartrate and Ibuprofen Tablets
Abuse of Hydrocodone bitartrate and ibuprofen tablets poses a risk of overdose and death. The risk is increased with concurrent use of Hydrocodone bitartrate and ibuprofen tablets with alcohol and/or other CNS depressants.

Parenteral drug abuse is commonly associated with transmission of infectious diseases such as hepatitis and HIV.

DEPENDENCE

Both tolerance and physical dependence can develop during use of opioid therapy.

Tolerance is a physiological state characterized by a reduced response to a drug after repeated administration (i.e., a higher dose of a drug is required to produce the same effect that was once obtained at a lower dose). Physical dependence is a state that develops as a result of a physiological adaptation in response to repeated drug use, manifested by withdrawal signs and symptoms after abrupt discontinuation or a significant dose reduction of a drug.

Withdrawal may be precipitated through the administration of drugs with opioid antagonist activity (e.g., naloxone, nalmefene), mixed agonist/antagonist analgesics (e.g., pentazocine, butorphanol, nalbuphine), or partial agonists (e.g., buprenorphine). Physical dependence may not occur to a clinically significant degree until after several days to weeks of continued use. Do not rapidly reduce or abruptly discontinue Hydrocodone bitartrate and ibuprofen tablets in a patient physically dependent on opioids. Rapid tapering of Hydrocodone bitartrate and ibuprofen tablets in a patient physically dependent on opioids may lead to serious withdrawal symptoms, uncontrolled pain, and suicide. Rapid discontinuation has also been associated with attempts to find other sources of opioid analgesics, which may be confused with drug-seeking for abuse.

When discontinuing Hydrocodone bitartrate and ibuprofen tablets, gradually taper the dosage using a patient-specific plan that considers the following: the dose of Hydrocodone bitartrate and ibuprofen tablets the patient has been taking, the duration of treatment, and the physical and psychological attributes of the patient. To improve the likelihood of a successful taper and minimize withdrawal symptoms, it is important that the opioid tapering schedule is agreed upon by the patient. In patients taking opioids for an extended period of time at high doses, ensure that a multimodal approach to pain management, including mental health support (if needed), is in place prior to initiating an opioid analgesic taper [see Dosage and Administration, and Warnings].

Infants born to mothers physically dependent on opioids will also be physically dependent and may exhibit respiratory difficulties and withdrawal signs [see Pregnancy].

OVERDOSAGE

Following an acute over dosage, toxicity may result from hydrocodone and/or ibuprofen.

Clinical Presentation

Hydrocodone Component

Acute overdose with opioids can be manifested by respiratory depression, somnolence progressing to stupor or coma, skeletal muscle flaccidity, cold and clammy skin, constricted pupils, and, in some cases, pulmonary edema, bradycardia, hypotension, hypoglycemia, partial or complete airway obstruction, atypical snoring, and death. Marked mydriasis rather than miosis may be seen with hypoxia in overdose situations [see CLINICAL PHARMACOLOGY]. Toxic leukoencephalopathy has been reported after opioid overdose and can present hours, days, or weeks after apparent recovery from the initial intoxication.

Ibuprofen Component

Symptoms following acute NSAID over dosages have been typically limited to lethargy, drowsiness, nausea, vomiting, and epigastric pain, which have been generally reversible with supportive care. Gastrointestinal bleeding has occurred (see WARNINGS: Gastrointestinal Bleeding, Ulceration, and Perforation). Hypertension, acute renal failure, respiratory depression, and coma have occurred, but were rare (see WARNINGS: Hypertension, Renal Toxicity and Hyperkalemia).

Treatment of Overdose

In case of overdose, priorities are the re-establishment of a patent and protected airway and institution of assisted or controlled ventilation, if needed. Employ other supportive measures (including oxygen and vasopressors) in the management of circulatory shock and pulmonary edema as indicated. Cardiac arrest or arrhythmias will require advanced life-support measures.

For clinically significant respiratory or circulatory depression secondary to opioid overdose, administer an opioid overdose reversal agent such as naloxone or nalmefene.

Because the duration of opioid reversal is expected to be less than the duration of action of hydrocodone, carefully monitor the patient until spontaneous respiration is reliably re-established. If the response to an opioid antagonist is suboptimal or only brief in nature, administer additional reversal agent as directed by the product’s prescribing information.

In an individual physically dependent on opioids, administration of the recommended usual dosage of the antagonist will precipitate an acute withdrawal syndrome. The severity of the withdrawal symptoms experienced will depend on the degree of physical dependence and the dose of the reversal agent administered. If a decision is made to treat serious respiratory depression in the physically dependent patient, administration of the reversal agent should be begin with care and by titration with smaller than usual doses of the antagonist.

Manage patients with symptomatic and supportive care following an NSAID over dosage. There are no specific antidotes. Consider emesis and/or activated charcoal (60 to 100 grams in adults, 1 to 2 grams per kg of body weight in pediatric patients) and/or osmotic cathartic in symptomatic patients seen within four hours of ingestion or in patients with a large overdose (5 to 10 times the recommended dosage). Forced diuresis, alkalinization of urine, hemodialysis, or hemoperfusion may not be useful due to high protein binding.

For additional information about over dosage treatment contact a poison control center (1-800-222-1222).

DOSAGE AND ADMINISTRATION

Hydrocodone Bitartrate and Ibuprofen Tablets should be prescribed only by healthcare professionals who are knowledgeable about the use of opioids and how to mitigate the associated risks.

Use the lowest effective dosage for the shortest duration of time consistent with individual patient treatment goals [see Warnings]. Because the risk of overdose increases as opioid doses increase, reserve titration to higher doses of Hydrocodone Bitartrate and Ibuprofen Tablets for patients in whom lower doses are insufficiently effective and in whom the expected benefits of using a higher dose opioid clearly outweigh the substantial risks.

Many acute pain conditions (e.g., the pain that occurs with a number of surgical procedures or acute musculoskeletal injuries) require no more than a few days of an opioid analgesic. Clinical guidelines on opioid prescribing for some acute pain conditions are available.

There is variability in the opioid analgesic dose and duration needed to adequately manage pain due both to the cause of pain and to individual patient factors. Initiate the dosing regimen for each patient individually, taking into account the patient’s underlying cause and severity of pain, prior analgesic treatment and response, and risk factors for addiction, abuse, and misuse [see Warnings].

Respiratory depression can occur at any time during opioid therapy, especially when initiating and following dosage increases with Hydrocodone Bitartrate and Ibuprofen Tablets. Consider this risk when selecting an initial dose and when making dose adjustments [see Warnings].

Patient Access to an Opioid Overdose Reversal Agent for the Emergency Treatment of Opioid Overdose
Inform patients and caregivers about opioid overdose reversal agents (e.g., naloxone, nalmefene). Discuss the importance of having access to an opioid overdose reversal agent, especially if the patient has risk factors for overdose (e.g., concomitant use of CNS depressants, a history of opioid use disorder, or prior opioid overdose) or if there are household members (including children) or other close contacts at risk for accidental ingestion or opioid overdose. The presence of risk factors for overdose should not prevent the management of pain in any patient [see WARNINGS; Addiction, Abuse, and Misuse; Life-Threatening Respiratory Depression; Risks from Concomitant Use with Benzodiazepines or Other CNS Depressants].
Discuss the options for obtaining an opioid overdose reversal agent (e.g., prescription, over-the-counter, or as part of a community-based program).
There are important differences among the opioid overdose reversal agents, such as route of administration, product strength, approved patient age range, and pharmacokinetics. Be familiar with these differences, as outlined in the approved labeling for those products, prior to recommending or prescribing such an agent.
Initial Dosage

Use of Hydrocodone Bitartrate and Ibuprofen Tablets as the First Opioid Analgesic

Initiate treatment with Hydrocodone Bitartrate and Ibuprofen Tablets at a dose of one tablet every 4 to 6 hours as needed for pain, at the lowest dose necessary to achieve adequate analgesia. Titrate the dose based upon the individual patient’s response to their initial dose of Hydrocodone Bitartrate and Ibuprofen Tablets. Dosage should not exceed 5 tablets in a 24-hour period.

The lowest effective dose or the longest dosing interval should be sought for each patient (see WARNINGS), especially in the elderly. After observing the initial response to therapy with hydrocodone bitartrate and ibuprofen tablets, the dose and frequency of dosing should be adjusted to suit the individual patient's need, without exceeding the total daily dose recommended.

Titration and Maintenance of Therapy

Individually titrate Hydrocodone Bitartrate and Ibuprofen Tablets to a dose that provides adequate analgesia and minimizes adverse reactions. Continually reevaluate patients receiving Hydrocodone Bitartrate and Ibuprofen Tablets to assess the maintenance of pain control, signs and symptoms of opioid withdrawal and other adverse reactions, as well as reassessing for the development of addiction, abuse, or misuse (see WARNINGS). Frequent communication is important among the prescriber, other members of the healthcare team, the patient, and the caregiver/family during periods of changing analgesic requirements, including initial titration.
If the level of pain increases after dosage stabilization, attempt to identify the source of increased pain before increasing the Hydrocodone Bitartrate and Ibuprofen Tablets dosage. If after increasing the dosage unacceptable opioid-related adverse reactions are observed (including an increase in pain after dosage increase), consider reducing the dosage [see Warnings]. Adjust the dosage to obtain an appropriate balance between management of pain and opioid- related adverse reactions.

Safe Reduction and Discontinuation of Hydrocodone Bitartrate and Ibuprofen Tablets

Do not abruptly discontinue Hydrocodone Bitartrate and Ibuprofen tablets in patients who may be physically dependent on opioids. Rapid reduction or abrupt discontinuation of opioid analgesics in patients who are physically dependent on opioids has resulted in serious withdrawal symptoms, uncontrolled pain, and suicide. Rapid reduction or abrupt discontinuation has also been associated with attempts to find other sources of opioid analgesics, which may be confused with drug-seeking for abuse. Patients may also attempt to treat their pain or withdrawal symptoms with illicit opioids, such as heroin, and other substances.

When a decision has been made to decrease the dose or discontinue therapy in an opioid-dependent patient taking Hydrocodone Bitartrate and Ibuprofen tablets there are a variety of factors that should be considered, including the total daily dose of opioid (including Hydrocodone Bitartrate and Ibuprofen tablets) the patient has been taking, the duration of treatment, the type of pain being treated, and the physical and psychological attributes of the patient. It is important to ensure ongoing care of the patient and to agree on an appropriate tapering schedule and follow-up plan so that patient and provider goals and expectations are clear and realistic. When opioid analgesics are being discontinued due to a suspected substance use disorder, evaluate and treat the patient, or refer for evaluation and treatment of the substance use disorder. Treatment should include evidence-based approaches, such as medication assisted treatment of opioid use disorder. Complex patients with co-morbid pain and substance use disorders may benefit from referral to a specialist.

There are no standard opioid tapering schedules that are suitable for all patients. Good clinical practice dictates a patient-specific plan to taper the dose of the opioid gradually. For patients on Hydrocodone Bitartrate and Ibuprofen tablets who are physically opioid-dependent, initiate the taper by a small enough increment (e.g., no greater than 10% to 25% of the total daily dose) to avoid withdrawal symptoms, and proceed with dose lowering at an interval of every 2 to 4 weeks. Patients who have been taking opioids for briefer periods of time may tolerate a more rapid taper.

It may be necessary to provide the patient with lower dosage strengths to accomplish a successful taper. Reassess the patient frequently to manage pain and withdrawal symptoms, should they emerge. Common withdrawal symptoms include restlessness, lacrimation, rhinorrhea, yawning, perspiration, chills, myalgia, and mydriasis. Other signs and symptoms also may develop, including irritability, anxiety, backache, joint pain, weakness, abdominal cramps, insomnia, nausea, anorexia, vomiting, diarrhea, or increased blood pressure, respiratory rate, or heart rate. If withdrawal symptoms arise, it may be necessary to pause the taper for a period of time or raise the dose of the opioid analgesic to the previous dose, and then proceed with a slower taper. In addition, evaluate patients for any changes in mood, emergence of suicidal thoughts, or use of other substances.

When managing patients taking opioid analgesics, particularly those who have been treated for a extended period of time and/or with high doses for chronic pain, ensure that a multimodal approach to pain management, including mental health support (if needed), is in place prior to initiating an opioid analgesic taper. A multimodal approach to pain management may optimize the treatment of chronic pain, as well as assist with the successful tapering of the opioid analgesic [see WARNINGS/ Withdrawal, DRUG ABUSE AND DEPENDENCE].

HOW SUPPLIED

Hydrocodone Bitartrate and Ibuprofen Tablets, 7.5 mg/200 mg are white to off-white, round, film coated tablets, debossed with “U13” on one side and plain on the other side.
Bottles of 10 NDC 13107-004-11
Bottles of 100 NDC 13107-004-01
Bottles of 500 NDC 13107-004-05
Bottles of 1,000 NDC 13107-004-99
Storage
Store at 20° to 25°C (68° to 77°F) [See USP Controlled Room Temperature].
Dispense in a tight, light-resistant container. Keep this and all medication out of the reach of children.
A Schedule II Controlled Drug Substance.
Store Hydrocodone Bitartrate and Ibuprofen Tablets securely and dispose of properly [see PRECAUTIONS/ Information for Patients].

Dispense with Medication Guide available at https://www.aurobindousa.com/medication-guides/

Distributed by:
Aurobindo Pharma USA, Inc.
279 Princeton-Hightstown Road
East Windsor, NJ 08520

Revised: 11/2025

MEDICATION GUIDE

HYDROCODONE BITARTRATE AND IBUPROFEN TABLETSCII

Hydrocodone Bitartrate and ibuprofen Tablets are:

- A strong prescription pain medicine that contains an opioid (narcotic) and a non-steroidal anti- inflammatory drug (NSAID), that is used to manage short-term (acute) pain, when other pain treatments such as non-opioid pain medicines do not treat your pain well enough or you cannot tolerate them.
- An opioid pain medicine can put you at risk for overdose and death. Even if you take your dose correctly as prescribed you are at risk for opioid addiction, abuse, and misuse that can lead to death.
- NSAIDs are used to treat pain, redness, swelling, and inflammation.

Important information about Hydrocodone Bitartrate And Ibuprofen Tablets:

- Get emergency help or call 911 right away if you take too much Hydrocodone Bitartrate And Ibuprofen Tablets (overdose). When you first start taking Hydrocodone Bitartrate and Ibuprofen Tablets, when your dose is changed, or if you take too much (overdose), serious or life-threatening breathing problems that can lead to death may occur. Ask your healthcare provider about naloxone or nalmefene that can be used in an emergency to reverse an opioid overdose,
- Taking Hydrocodone Bitartrate and Ibuprofen Tablets with other opioid medicines, benzodiazepines, gabapentinoids (gabapentin or pregabalin) alcohol, or other central nervous system depressants (including street drugs) can cause severe drowsiness, decreased awareness, breathing problems, coma, and death.
- Never give anyone else your Hydrocodone Bitartrate and Ibuprofen Tablets. They could die from taking it. Selling or giving away Hydrocodone Bitartrate and Ibuprofen Tablets are against the law.
- Store Hydrocodone Bitartrate and Ibuprofen Tablets securely, out of sight and reach of children, and in a location not accessible by others, including visitors to the home.

Hydrocodone Bitartrate And Ibuprofen Tablets contains an NSAID. NSAIDs can cause serious side effects, including:

- Increased risk of a heart attack or stroke that can lead to death. This risk may happen early in treatment and may increase:

- with increasing doses of medicine containing NSAIDs
- with longer use of medicine containing NSAIDs

Do not take NSAIDS right before or after a heart surgery called a “coronary artery bypass graft (CABG).”
Avoid taking NSAIDS after a recent heart attack, unless your healthcare provider tells you to. You may have an increased risk of another heart attack if you take NSAIDs after a recent heart attack.

- Increased risk of bleeding, ulcers, and tears (perforation) of the esophagus (tube leading from the mouth to the stomach), stomach and intestines:
  - any time during use
  - without warning symptoms
  - that may cause death
- The risk of getting an ulcer or bleeding increases with:
  - past history of stomach ulcers, or stomach or intestinal bleeding with use of NSAIDs
  - increasing doses of NSAIDS
  - longer use of NSAIDS
  - smoking
  - drinking alcohol
  - taking medicines called “corticosteroids,” “anticoagulants,” “SSRIs,” or “SNRIs”
  - older age
  - poor health
  - advanced liver disease
  - bleeding problems

Do not take Hydrocodone Bitartrate And Ibuprofen Tablets:

- if you have severe asthma, trouble breathing, or other lung problems.
- if you have a bowel blockage or have narrowing of the stomach or intestines.
- if you have had an asthma attack, hives, or other allergic reaction with aspirin, other NSAIDs, or opioid medicine.
- right before or after heart bypass surgery.

Before taking Hydrocodone Bitartrate And Ibuprofen Tablets, tell your healthcare provider if you have a history of:
• head injury or seizures • liver, kidney, or thyroid problems
• problems urinating • pancreas or gallbladder problems
• high blood pressure • asthma
• abuse of street or prescription drugs, alcohol addiction, opioid overdose, or mental health problems.
Tell your healthcare provider if you are:

- noticing your pain getting worse. If your pain gets worse after you take Hydrocodone Bitartrate and Ibuprofen tablets do not take more of Hydrocodone Bitartrate and Ibuprofen Tablets without first talking to your Healthcare provider. Talk to your healthcare provider if the pain that you have increases, if you feel more sensitive to pain, or if you have new pain after taking Hydrocodone Bitartrate and Ibuprofen Tablets.
- Pregnantor planning to become pregnant. Use of hydrocode Bitartrate and Ibuprofen Tablets for an extended period of time during pregnancy can cause withdrawal symptoms in your newborn baby that could be life-threatening if not recognized and treated.
- Breastfeeding or planning to breastfeed. Hydrocodone Bitartrate and Ibuprofen Tabletspasses into breast milk and may harm your baby.
- develop any type of rash or fever. Contact your healthcare provider as soon as possible and stop taking Hydrocodone Bitartrate and Ibuprofen Tablets.
- living in a household where there are small children or someone who has abused street or prescription drugs
- taking prescription or over-the-counter medicines, vitamins, or herbal supplements. Taking Hydrocodone Bitartrate and Ibuprofen Tablets with certain other medicines can cause serious side effects that could lead to death.

When taking Hydrocodone Bitartrate And Ibuprofen Tablets:

- Do not change your dose. Take Hydrocodone Bitartrate and Ibuprofen Tablets exactly as prescribed by your healthcare provider.
- For acute (short-term) pain, you may only need to take Hydrocodone Bitartrate and Ibuprofen Tablets for a few days. You may have some Hydrocodone Bitartrate and Ibuprofen Tablets left over that you did not use, See disposal information at the bottom of this section for directions on how to safely throw away (dispose of) Hydrocodone Bitartrate and Ibuprofen Tablets.
- Use the lowest dose possible for the shortest time needed.
- Take your prescribed dose every 4 to 6 hours, as needed. Do not take more than your prescribed dose. If you miss a dose, take your next dose at your usual time.
- Call your healthcare provider if the dose you are taking does not control your pain.
- If you have been taking Hydrocodone Bitartrate and Ibuprofen Tablets regularly, do not stop taking it without talking to your healthcare provider.
- Dispose of expired, unwanted, or unused hydrocodone bitartrate and ibuprofen tablets by promptly flushing down the toilet, if a drug take-back option is not readily available.Visit www.fda.gov/drugdisposal for additional information on disposal of unused medicines.

While taking Hydrocodone Bitartrate And Ibuprofen Tablets DO NOT:
• drive or operate heavy machinery, until you know how it affects you. Hydrocodone Bitartrate And Ibuprofen Tablets can make you sleepy, dizzy, or lightheaded.
• drink alcohol or use prescription or over-the-counter medicines that contain alcohol. Using products containing alcohol during treatment with Hydrocodone Bitartrate And Ibuprofen Tablets may cause you to overdose and die.

The possible side effects of Hydrocodone Bitartrate And Ibuprofen Tablets:

- constipation, diarrhea, gas, heartburn, nausea, sleepiness, vomiting, tiredness, headache, dizziness, abdominal pain, rash, or fever, heart attack, stroke, new or worse high blood pressure, heart failure, liver problems including liver failure, kidney problems including kidney failure, bleeding and ulcers in the stomach and intestine, low red blood cells (anemia), life-threatening skin reactions, life- threatening allergic reactions, asthma attacks in people who have asthma. Call your healthcare provider if you have any of these symptoms and they are severe.

Get emergency medical help or call 911 right away if you have:
• trouble breathing or shortness of breath • agitation
• fast heartbeat • high body temperature
• chest pain • trouble walking
• swelling of your face, tongue, or throat • stiff muscles
• extreme drowsiness • mental changes such as confusion
• lightheadedness when changing positions • weakness in one part or side of your body
• a fainting spell • slurred speech
Stop Hydrocodone Bitartrate And Ibuprofen Tablets and call your healthcare provider right away if you have any of the followingsymptoms:
• nausea • flu-like symptoms
• more tired or weaker than usual • vomit blood
• diarrhea • there is blood in your bowel movement or it is black and sticky like tar
• itching • unusual weight gain
• your skin or eyes look yellow • skin rash or blisters with fever
• indigestion or stomach pain • swelling of the arms and legs, hands and feet
These are not all the possible side effects of Hydrocodone Bitartrate And Ibuprofen Tablets. Call your healthcare provider for medical advice about side effects. You may report side effects to FDA at 1-800-FDA-1088. For more information go todailymed.nlm.nih.gov. Other information:
• Aspirin is an NSAID medicine, but it does not increase the chance of a heart attack. Aspirin can cause bleeding in the brain, stomach, and intestines. Aspirin can also cause ulcers in the stomach and intestines.
• Do not take other NSAID medicines, even those sold in lower doses without a prescription (over-the-counter) while taking Hydrocodone bitartrate and ibuprofen tablets. NSAIDs may be present in over-the-counter medications for treatment of colds, fever, or insomnia.

This Medication Guide has been approved by the U.S. Food and Drug Administration.
Dispense with Medication Guide available at https://www.aurobindousa.com/medication-guides/
Distributed by:
Aurobindo Pharma USA, Inc.
279 Princeton-Hightstown Road
East Windsor, NJ 08520

Revised: 08/2025

PACKAGE LABEL.PRINCIPAL DISPLAY PANEL - 7.5 mg/200 mg (100's Bottle)

NDC 13107-004-01
Hydrocodone Bitartrate and Ibuprofen Tablets CII
7.5 mg/200 mg
Pharmacist: Please dispense with medication
guide provided separately
Rx only 100 Tablets